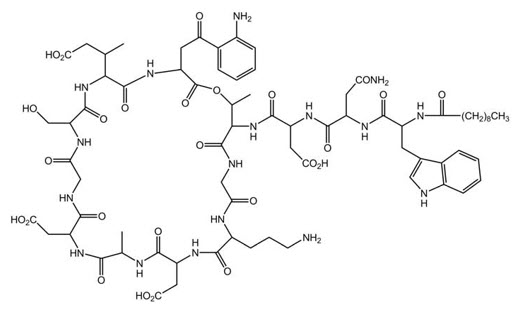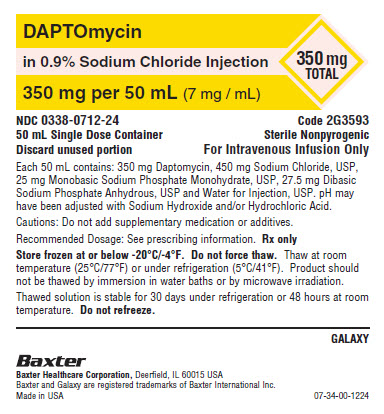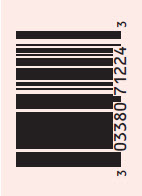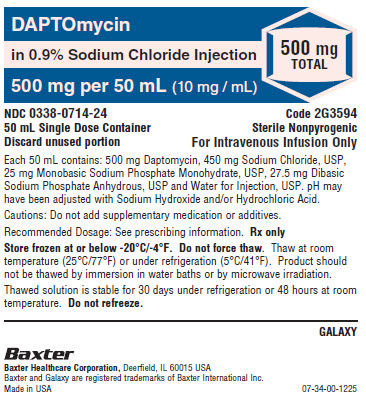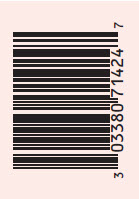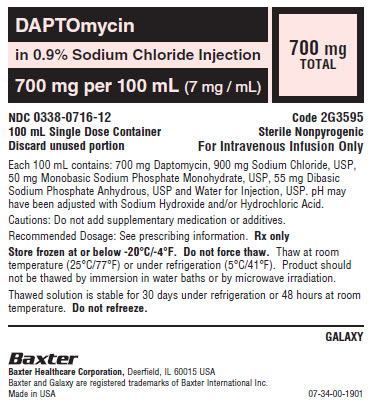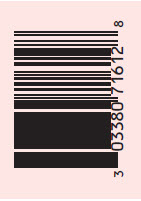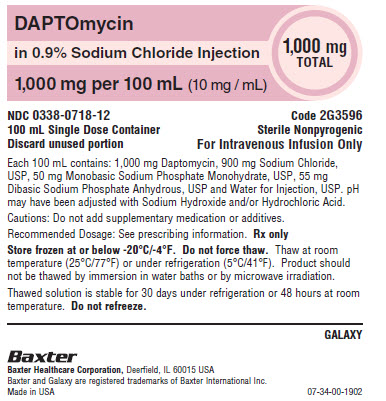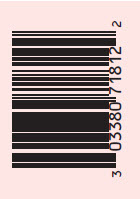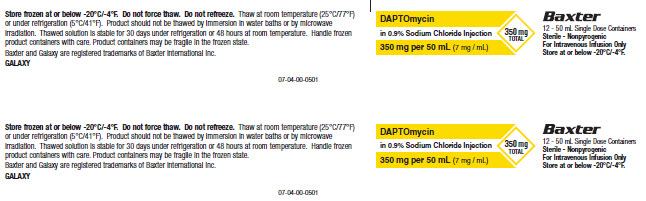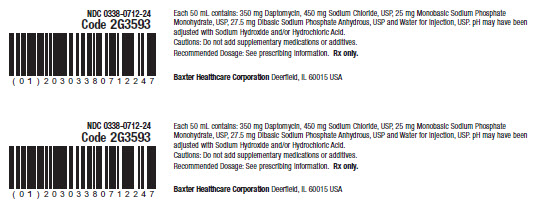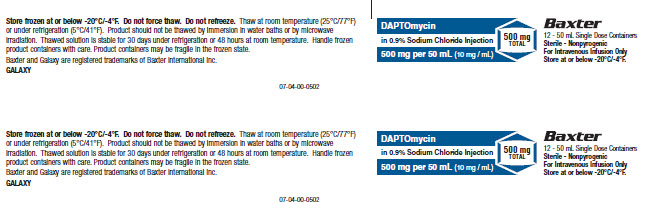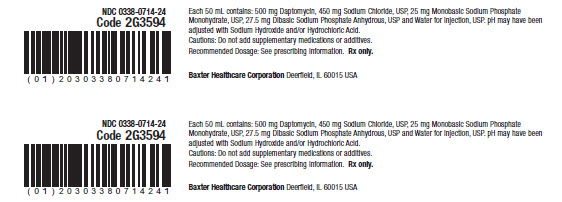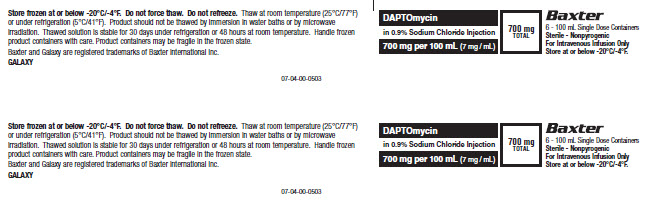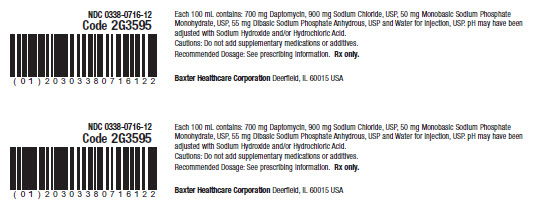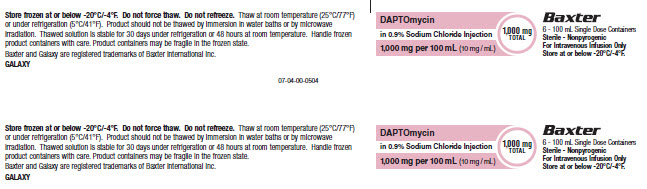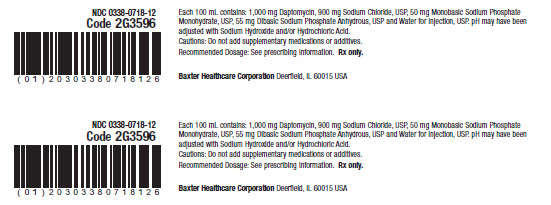 DRUG LABEL: Daptomycin in Sodium Chloride
NDC: 0338-0712 | Form: INJECTION, SOLUTION
Manufacturer: Baxter Healthcare Corporation
Category: prescription | Type: HUMAN PRESCRIPTION DRUG LABEL
Date: 20250430

ACTIVE INGREDIENTS: DAPTOMYCIN 350 mg/50 mL
INACTIVE INGREDIENTS: SODIUM CHLORIDE 450 mg/50 mL; SODIUM PHOSPHATE, MONOBASIC, MONOHYDRATE 25 mg/50 mL; SODIUM PHOSPHATE, DIBASIC, ANHYDROUS 27.5 mg/50 mL; WATER

HIGHLIGHTS OF PRESCRIBING INFORMATION

These highlights do not include all the information needed to use DAPTOMYCIN IN SODIUM CHLORIDE INJECTION safely and effectively. See full prescribing information for DAPTOMYCIN IN SODIUM CHLORIDE INJECTION.
DAPTOMYCIN IN SODIUM CHLORIDE injection, for intravenous use
Initial U.S. Approval: 2003

1 INDICATIONS AND USAGE

Daptomycin in Sodium Chloride Injection is a lipopeptide antibacterial indicated for the treatment of:

- Complicated skin and skin structure infections (cSSSI) in adult and pediatric patients (1 to 17 years of age) for whom appropriate dosing can be achieved (1.1) and,
- Staphylococcus aureus bloodstream infections (bacteremia), in adult patients for whom appropriate dosing can be achieved, including those with right-sided infective endocarditis, (1.2)
- Staphylococcus aureus bloodstream infections (bacteremia) in pediatric patients (1 to 17 years of age) for whom appropriate dosing can be achieved. (1.3)

Limitations of Use

- Daptomycin in Sodium Chloride Injection is not indicated for the treatment of pneumonia. (1.4)
- Daptomycin in Sodium Chloride Injection is not indicated for the treatment of left-sided infective endocarditis due to S. aureus. (1.4)
- Daptomycin in Sodium Chloride Injection is not recommended in pediatric patients younger than one year of age due to the risk of potential effects on muscular, neuromuscular, and/or nervous systems (either peripheral and/or central) observed in neonatal dogs. (1.4)

To reduce the development of drug-resistant bacteria and maintain the effectiveness of Daptomycin in Sodium Chloride Injection and other antibacterial drugs, Daptomycin in Sodium Chloride Injection should be used to treat or prevent infections that are proven or strongly suspected to be caused by bacteria. (1.5)

2 DOSAGE AND ADMINISTRATION

If a dose of Daptomycin in Sodium Chloride Injection is required that does not equal 350 mg, 500 mg, 700 mg or 1,000 mg, this product is not recommended for use and an alternative formulation of daptomycin should be considered. (2.1)

Adult Patients

- Administer to adult patients intravenously by infusion over a 30-minute period. (2.1, 2.7)
- Recommended dosage regimen for adult patients (2.2, 2.4, 2.6):

Creatinine Clearance (CLCR) | Dosage Regimen
Creatinine Clearance (CLCR) | cSSSI For 7 to 14 days | S. aureus Bacteremia For 2 to 6 weeks
≥30 mL/min | 4 mg/kg once every 24 hours | 6 mg/kg once every 24 hours
<30 mL/min, including hemodialysis and CAPD | 4 mg/kg once every 48 hours* | 6 mg/kg once every 48 hours*
*Administered following hemodialysis on hemodialysis days.

Pediatric Patients

- Administer to pediatric patients intravenously by infusion over a 30- or 60-minute period, based on age. (2.1, 2.7)
- Recommended dosage regimen for pediatric patients (1 to 17 years of age) with cSSSI, based on age (2.3):

Age group | Dosage* | Duration of therapy
12 to 17 years | 5 mg/kg once every 24 hours infused over 30 minutes | Up to 14 days
7 to 11 years | 7 mg/kg once every 24 hours infused over 30 minutes | Up to 14 days
2 to 6 years | 9 mg/kg once every 24 hours infused over 60 minutes | Up to 14 days
1 to less than 2 years | 10 mg/kg once every 24 hours infused over 60 minutes | Up to 14 days
*Recommended dosage is for pediatric patients (1 to 17 years of age) with normal renal function. Dosage adjustment for pediatric patients with renal impairment has not been established.

- Recommended dosage regimen for pediatric patients (1 to 17 years of age) with S. aureus bacteremia, based on age (2.5):

Age group | Dosage* | Duration of therapy
12 to 17 years | 7 mg/kg once every 24 hours infused over 30 minutes | Up to 42 days
7 to 11 years | 9 mg/kg once every 24 hours infused over 30 minutes | Up to 42 days
1 to 6 years | 12 mg/kg once every 24 hours infused over 60 minutes | Up to 42 days
*Recommended dosage is for pediatric patients (1 to 17 years of age) with normal renal function. Dosage adjustment for pediatric patients with renal impairment has not been established.

3 DOSAGE FORMS AND STRENGTHS

- Injection: 350 mg/50 mL (7 mg/mL), 500 mg/50 mL (10 mg/mL), 700 mg/100 mL (7 mg/mL), and 1,000 mg/100 mL (10 mg/mL) in single-dose GALAXY Container. (3)

4 CONTRAINDICATIONS

- Known hypersensitivity to daptomycin (4)

5 WARNINGS AND PRECAUTIONS

- Anaphylaxis/hypersensitivity reactions (including life-threatening): Discontinue Daptomycin in Sodium Chloride Injection and treat signs/symptoms. (5.1)
- Myopathy and rhabdomyolysis: Monitor CPK levels and follow muscle pain or weakness; if elevated CPK or myopathy occurs, consider discontinuation of Daptomycin in Sodium Chloride Injection. (5.2)
- Eosinophilic pneumonia: Discontinue Daptomycin in Sodium Chloride Injection and consider treatment with systemic steroids. (5.3)
- Drug Reaction with Eosinophilia and Systemic Symptoms (DRESS): Discontinue Daptomycin in Sodium Chloride Injection and institute appropriate treatment. (5.4)
- Tubulointerstitial Nephritis (TIN): Discontinue Daptomycin in Sodium Chloride Injection and institute appropriate treatment. (5.5)
- Peripheral neuropathy: Monitor for neuropathy and consider discontinuation. (5.6)
- Potential nervous system and/or muscular system effects in pediatric patients younger than 12 months: Avoid use of Daptomycin in Sodium Chloride Injection in this age group. (5.7)
- Clostridioides difficile–associated diarrhea: Evaluate patients if diarrhea occurs. (5.8)
- Persisting or relapsing S. aureus bacteremia/endocarditis: Perform susceptibility testing and rule out sequestered foci of infection. (5.9)
- Decreased efficacy was observed in adult patients with moderate baseline renal impairment. (5.10)

6 ADVERSE REACTIONS

- Adult cSSSI Patients: The most common adverse reactions that occurred in ≥2% of adult cSSSI patients receiving daptomycin for injection 4 mg/kg were diarrhea, headache, dizziness, rash, abnormal liver function tests, elevated creatine phosphokinase (CPK), urinary tract infections, hypotension, and dyspnea. (6.1)
- Pediatric cSSSI Patients: The most common adverse reactions that occurred in ≥2% of pediatric patients receiving daptomycin for injection were diarrhea, vomiting, abdominal pain, pruritus, pyrexia, elevated CPK, and headache. (6.1)
- Adult S. aureus bacteremia/endocarditis Patients: The most common adverse reactions that occurred in ≥5% of S. aureus bacteremia/endocarditis patients receiving daptomycin for injection 6 mg/kg were sepsis, bacteremia, abdominal pain, chest pain, edema, pharyngolaryngeal pain, pruritus, increased sweating, insomnia, elevated CPK, and hypertension. (6.1)
- Pediatric S. aureus bacteremia Patients: The most common adverse reactions that occurred in ≥5% of pediatric patients receiving daptomycin for injection were vomiting and elevated CPK. (6.1)

To report SUSPECTED ADVERSE REACTIONS, contact Baxter Healthcare Corporation at 1-866-888-2472 or FDA at 1-800-FDA-1088 or www.fda.gov/medwatch.

FULL PRESCRIBING INFORMATION

1 INDICATIONS AND USAGE

1.1 Complicated Skin and Skin Structure Infections (cSSSI)

Daptomycin in Sodium Chloride Injection is indicated for the treatment of adult and pediatric patients (1 to 17 years of age) for whom appropriate dosing can be achieved, with complicated skin and skin structure infections (cSSSI) caused by susceptible isolates of the following Gram-positive bacteria: Staphylococcus aureus (including methicillin-resistant isolates), Streptococcus pyogenes, Streptococcus agalactiae, Streptococcus dysgalactiae subsp. equisimilis, and Enterococcus faecalis (vancomycin-susceptible isolates only).

1.2 Staphylococcus aureus Bloodstream Infections (Bacteremia) in Adult Patients, Including Those with Right-Sided Infective Endocarditis, Caused by Methicillin-Susceptible and Methicillin-Resistant Isolates

Daptomycin in Sodium Chloride Injection is indicated for the treatment of adult patients for whom appropriate dosing can be achieved, with Staphylococcus aureus bloodstream infections (bacteremia), including adult patients with right-sided infective endocarditis, caused by methicillin-susceptible and methicillin-resistant isolates.

1.3 Staphylococcus aureus Bloodstream Infections (Bacteremia) in Pediatric Patients (1 to 17 Years of Age)

Daptomycin in Sodium Chloride Injection is indicated for the treatment of pediatric patients (1 to 17 years of age) for whom appropriate dosing can be achieved with Staphylococcus aureus bloodstream infections (bacteremia).

1.4 Limitations of Use

Daptomycin in Sodium Chloride Injection is not indicated for the treatment of pneumonia.

Daptomycin in Sodium Chloride Injection is not indicated for the treatment of left-sided infective endocarditis due to S. aureus. The clinical trial of daptomycin for injection in adult patients with S. aureus bloodstream infections included limited data from patients with left-sided infective endocarditis; outcomes in these patients were poor [see Clinical Studies (14.2)]. Daptomycin for injection has not been studied in patients with prosthetic valve endocarditis.

Daptomycin in Sodium Chloride Injection is not recommended in pediatric patients younger than 1 year of age due to the risk of potential effects on muscular, neuromuscular, and/or nervous systems (either peripheral and/or central) observed in neonatal dogs [see Warnings and Precautions (5.7) and Nonclinical Toxicology (13.2)].

1.5 Usage

Appropriate specimens for microbiological examination should be obtained in order to isolate and identify the causative pathogens and to determine their susceptibility to daptomycin.

To reduce the development of drug-resistant bacteria and maintain the effectiveness of Daptomycin in Sodium Chloride Injection and other antibacterial drugs, Daptomycin in Sodium Chloride Injection should be used only to treat or prevent infections that are proven or strongly suspected to be caused by susceptible bacteria.

When culture and susceptibility information is available, it should be considered in selecting or modifying antibacterial therapy. In the absence of such data, local epidemiology and susceptibility patterns may contribute to the empiric selection of therapy. Empiric therapy may be initiated while awaiting test results.

2 DOSAGE AND ADMINISTRATION

2.1 Important Administration Duration Instructions

If a dose of Daptomycin in Sodium Chloride Injection is required that does not equal 350 mg, 500 mg, 700 mg or 1,000 mg, this product is not recommended for use and an alternative formulation of daptomycin should be considered.

Adult Patients:

Administer the appropriate dose of Daptomycin in Sodium Chloride Injection to adult patients by intravenous infusion over a thirty (30) minute period [see Dosage and Administration (2.2, 2.4, 2.7)].

Pedatric Patients (1 to 17 Years of Age)

- Pediatric Patients 7 to 17 years of Age: Administer Daptomycin in Sodium Chloride Injection intravenously by infusion over a 30-minute period [see Dosage and Administration (2.3, 2.5, 2.7)].
- Pediatric Patients 1 to 6 years of Age: Administer Daptomycin in Sodium Chloride Injection intravenously by infusion over a 60-minute period [see Dosage and Administration (2.3, 2.5, 2.7)].

2.2 Dosage in Adults for cSSSI

Administer Daptomycin in Sodium Chloride Injection 4 mg/kg to adult patients intravenously once every 24 hours for 7 to 14 days.

2.3 Dosage in Pediatric Patients (1 to 17 Years of Age) for cSSSI

If a dose of Daptomycin in Sodium Chloride Injection is required that does not equal 350 mg, 500 mg, 700 mg or 1,000 mg, this product is not recommended for use and an alternative formulation of daptomycin should be considered. The recommended dosage regimens based on age for pediatric patients with cSSSI are shown in Table 1. Administer Daptomycin in Sodium Chloride Injection intravenously once every 24 hours for up to 14 days.

Table 1. Recommended Dosage of Daptomycin in Sodium Chloride Injection in Pediatric Patients (1 to 17 Years of Age) with cSSSI, Based on Age
Age Range | Dosage Regimen* | Duration of therapy
12 to 17 years | 5 mg/kg once every 24 hours infused over 30 minutes | Up to 14 days
7 to 11 years | 7 mg/kg once every 24 hours infused over 30 minutes | Up to 14 days
2 to 6 years | 9 mg/kg once every 24 hours infused over 60 minutes | Up to 14 days
1 to less than 2 years | 10 mg/kg once every 24 hours infused over 60 minutes | Up to 14 days
*Recommended dosage regimen is for pediatric patients (1 to 17 years of age) with normal renal function. Dosage adjustment for pediatric patients with renal impairment has not been established.

2.4 Dosage in Adult Patients with Staphylococcus aureus Bloodstream Infections (Bacteremia), Including Those with Right-Sided Infective Endocarditis, Caused by Methicillin-Susceptible and Methicillin-Resistant Isolates

Administer Daptomycin in Sodium Chloride Injection 6 mg/kg to adult patients intravenously once every 24 hours for 2 to 6 weeks. There are limited safety data for the use of daptomycin for injection for more than 28 days of therapy. In the Phase 3 trial, there were a total of 14 adult patients who were treated with daptomycin for injection for more than 28 days.

2.5 Dosage in Pediatric Patients (1 to 17 Years of Age) with Staphylococcus aureus Bloodstream Infections (Bacteremia)

If a dose of Daptomycin in Sodium Chloride Injection is required that does not equal 350 mg, 500 mg, 700 mg or 1,000 mg, this product is not recommended for use and an alternative formulation of daptomycin should be considered. The recommended dosage regimens based on age for pediatric patients with S. aureus bloodstream infections (bacteremia) are shown in Table 2. Administer Daptomycin in Sodium Chloride Injection intravenously once every 24 hours for up to 42 days.

Table 2. Recommended Dosage of Daptomycin in Sodium Chloride Injection in Pediatric Patients (1 to 17 Years of Age) with S. aureus Bacteremia, Based on Age
Age | Dosage* | Duration of therapy
12 to 17 years | 7 mg/kg once every 24 hours infused over 30 minutes | Up to 42 days
7 to 11 years | 9 mg/kg once every 24 hours infused over 30 minutes | Up to 42 days
1 to 6 years | 12 mg/kg once every 24 hours infused over 60 minutes | Up to 42 days
*Recommended dosage is for pediatric patients (1 to 17 years of age) with normal renal function. Dosage adjustment for pediatric patients with renal impairment has not been established.

2.6 Dosage in Patients with Renal Impairment

Adult Patients:

No dosage adjustment is required in adult patients with creatinine clearance (CLCR) greater than or equal to 30 mL/min. The recommended dosage regimen for Daptomycin in Sodium Chloride Injection in adult patients with CLCR less than 30 mL/min, including adult patients on hemodialysis or continuous ambulatory peritoneal dialysis (CAPD), is 4 mg/kg (cSSSI) or 6 mg/kg (S. aureus bloodstream infections) once every 48 hours (Table 3). When possible, Daptomycin in Sodium Chloride Injection should be administered following the completion of hemodialysis on hemodialysis days [see Warnings and Precautions (5.2, 5.10), Use in Specific Populations (8.6), and Clinical Pharmacology (12.3)].

Table 3. Recommended Dosage of Daptomycin in Sodium Chloride Injection in Adult Patients
Creatinine Clearance (CLCR) | Dosage Regimen in Adults
Creatinine Clearance (CLCR) | cSSSI | S. aureus Bloodstream Infections
Greater than or equal to 30 mL/min | 4 mg/kg once every 24 hours | 6 mg/kg once every 24 hours
Less than 30 mL/min, including hemodialysis and CAPD | 4 mg/kg once every 48 hours* | 6 mg/kg once every 48 hours*
*When possible, administer Daptomycin in Sodium Chloride Injection following the completion of hemodialysis on hemodialysis days.

Pediatric Patients:

The dosage regimen for Daptomycin in Sodium Chloride Injection in pediatric patients with renal impairment has not been established.

2.7 Preparation and Administration of Daptomycin in Sodium Chloride Injection

Thawing of Plastic Container

- Thaw frozen container at room temperature 20°C to 25°C (68°F to 77°F) or under refrigeration 2°C to 8°C (36°F to 46°F). Product should not be thawed by immersion in water baths or by microwave irradiation. Do not force thaw.
- No further dilution is necessary.
- Check for minute leaks by squeezing container firmly. If leaks are detected, discard solution as sterility may be impaired.
- Do not add supplementary medication.
- The container should be visually inspected. If the outlet port protector is damaged, detached, or not present, discard container as solution path sterility may be impaired.
- Thaw and equilibrate container to a room temperature.
- Agitate after solution has reached room temperature. If after visual inspection the solution remains cloudy or if an insoluble precipitate is noted or if any seals are not intact, the container should be discarded.
- Solution should be clear and slightly yellow in color.
- The thawed solution is stable for 30 days under refrigeration (5°C/41°F) or 48 hours at room temperature (25°C/77°F). Do not refreeze thawed antibacterial drugs.

Preparation for Administration

- Suspend container from support.
- Remove protector from outlet port at bottom of container.
- Attach Intravenous administration set to outlet port. Refer to the manufacturer’s instructions accompanying the administration set for complete directions.

Administration Instructions

Parenteral drug products should be inspected visually for particulate matter and discoloration prior to administration, whenever solution and container permit.

Adults

Intravenous Infusion over a period of 30 minutes

- For intravenous infusion over a period of 30 minutes in adult patients: The appropriate dose of Daptomycin in Sodium Chloride Injection should be used, based on patient weight.

Pediatric Patients (1 to 17 Years of Age)

Intravenous Infusion over a period of 30 or 60 minutes

- For Intravenous infusion over a period of 60 minutes in pediatric patients 1 to 6 years of age: The appropriate dose of Daptomycin in Sodium Chloride Injection should be used, based on patient weight. The infusion rate should be maintained at 0.83 mL/min for a 50 mL GALAXY container and 1.67 mL/min for a 100 mL GALAXY container over the 60-minute period.
- For Intravenous infusion over a period of 30 minutes in pediatric patients 7 to 17 years of age: The appropriate dose of Daptomycin in Sodium Chloride Injection should be used, based on patient weight. The infusion rate should be maintained at 1.67 mL/min for a 50 mL GALAXY container and 3.33 mL/min for a 100 mL GALAXY container over the 30-minute period.

Do not exceed the In-Use storage conditions of Daptomycin in Sodium Chloride Injection described below. Discard unused portions of Daptomycin in Sodium Chloride Injection.

In-Use Storage Conditions for Daptomycin in Sodium Chloride Injection

The thawed solution is stable for 30 days under refrigeration (5°C/41°F) or 48 hours at 25°C/77°F. Do not refreeze thawed antibacterial drugs.

2.8 Incompatibilities

Because only limited data are available on the compatibility of daptomycin with other intravenous substances, additives and other medications should not be added to Daptomycin in Sodium Chloride Injection ready to use infusion bags, or infused simultaneously with Daptomycin in Sodium Chloride Injection through the same IV line. If the same intravenous line is used for sequential infusion of different drugs, the line should be flushed with a compatible intravenous solution before and after infusion with Daptomycin in Sodium Chloride Injection.

3 DOSAGE FORMS AND STRENGTHS

Injection: Daptomycin in Sodium Chloride injection is a frozen, premixed, iso-osmotic, sterile, nonpyrogenic solution in the GALAXY container.

- 350 mg/50 mL (7 mg/mL): Each 50 mL single-dose GALAXY container contains 350 mg daptomycin in sodium chloride.
- 500 mg/50 mL (10 mg/mL): Each 50 mL single-dose GALAXY container contains 500 mg daptomycin in sodium chloride.
- 700 mg/100 mL (7 mg/mL): Each 100 mL single-dose GALAXY container contains 700 mg daptomycin in sodium chloride.
- 1,000 mg/100 mL (10 mg/mL): Each 100 mL single-dose GALAXY container contains 1,000 mg daptomycin in sodium chloride.

4 CONTRAINDICATIONS

Daptomycin in Sodium Chloride Injection is contraindicated in patients with known hypersensitivity to daptomycin [see Warnings and Precautions (5.1)].

5 WARNINGS AND PRECAUTIONS

5.1 Anaphylaxis/Hypersensitivity Reactions

Anaphylaxis/hypersensitivity reactions have been reported with the use of antibacterial agents, including daptomycin for injection, and may be life-threatening. If an allergic reaction to Daptomycin in Sodium Chloride Injection occurs, discontinue the drug and institute appropriate therapy [see Adverse Reactions (6.2)].

5.2 Myopathy and Rhabdomyolysis

Myopathy, defined as muscle aching or muscle weakness in conjunction with increases in creatine phosphokinase (CPK) values to greater than 10 times the upper limit of normal (ULN), has been reported with the use of daptomycin for injection. Rhabdomyolysis, with or without acute renal failure, has been reported [see Adverse Reactions (6.2)].

Patients receiving Daptomycin in Sodium Chloride Injection should be monitored for the development of muscle pain or weakness, particularly of the distal extremities. In patients who receive Daptomycin in Sodium Chloride Injection, CPK levels should be monitored weekly, and more frequently in patients who received recent prior or concomitant therapy with an HMG-CoA reductase inhibitor or in whom elevations in CPK occur during treatment with Daptomycin in Sodium Chloride Injection.

In adult patients with renal impairment, both renal function and CPK should be monitored more frequently than once weekly [see Use in Specific Populations (8.6) and Clinical Pharmacology (12.3)].

In Phase 1 studies and Phase 2 clinical trials in adults, CPK elevations appeared to be more frequent when daptomycin for injection was dosed more than once daily. Therefore, Daptomycin in Sodium Chloride Injection should not be dosed more frequently than once a day.

Daptomycin in Sodium Chloride Injection should be discontinued in patients with unexplained signs and symptoms of myopathy in conjunction with CPK elevations to levels >1,000 U/L (~5× ULN), and in patients without reported symptoms who have marked elevations in CPK, with levels >2,000 U/L (≥10× ULN).

In addition, consideration should be given to suspending agents associated with rhabdomyolysis, such as HMG-CoA reductase inhibitors, temporarily in patients receiving Daptomycin in Sodium Chloride Injection [see Drug Interactions (7.1)].

5.3 Eosinophilic Pneumonia

Eosinophilic pneumonia has been reported in patients receiving daptomycin for injection [see Adverse Reactions (6.2)]. In reported cases associated with daptomycin for injection, patients developed fever, dyspnea with hypoxic respiratory insufficiency, and diffuse pulmonary infiltrates or organizing pneumonia. In general, patients developed eosinophilic pneumonia 2 to 4 weeks after starting daptomycin for injection and improved when daptomycin for injection was discontinued and steroid therapy was initiated. Recurrence of eosinophilic pneumonia upon re-exposure has been reported. Patients who develop these signs and symptoms while receiving Daptomycin in Sodium Chloride Injection should undergo prompt medical evaluation, and Daptomycin in Sodium Chloride Injection should be discontinued immediately. Treatment with systemic steroids is recommended.

5.4 Drug Reaction with Eosinophilia and Systemic Symptoms (DRESS)

DRESS has been reported in post-marketing experience with daptomycin for injection [see Adverse Reactions (6.2)]. Patients who develop skin rash, fever, peripheral eosinophilia, and systemic organ (for example, hepatic, renal, pulmonary) impairment while receiving Daptomycin in Sodium Chloride Injection should undergo medical evaluation. If DRESS is suspected, discontinue Daptomycin in Sodium Chloride Injection promptly and institute appropriate treatment.

5.5 Tubulointerstitial Nephritis (TIN)

TIN has been reported in post-marketing experience with daptomycin for injection [see Adverse Reactions (6.2)]. Patients who develop new or worsening renal impairment while receiving Daptomycin in Sodium Chloride Injection should undergo medical evaluation. If TIN is suspected, discontinue Daptomycin in Sodium Chloride Injection promptly and institute appropriate treatment.

5.6 Peripheral Neuropathy

Cases of peripheral neuropathy have been reported during the daptomycin for injection postmarketing experience [see Adverse Reactions (6.2)]. Therefore, physicians should be alert to signs and symptoms of peripheral neuropathy in patients receiving Daptomycin in Sodium Chloride Injection. Monitor for neuropathy and consider discontinuation.

5.7 Potential Nervous System and/or Muscular System Effects in Pediatric Patients Younger than 12 Months

Avoid use of Daptomycin in Sodium Chloride Injection in pediatric patients younger than 12 months due to the risk of potential effects on muscular, neuromuscular, and/or nervous systems (either peripheral and/or central) observed in neonatal dogs with intravenous daptomycin [see Nonclinical Toxicology (13.2)].

5.8 Clostridioides difficile-Associated Diarrhea

Clostridioides difficile–associated diarrhea (CDAD) has been reported with the use of nearly all systemic antibacterial agents, including daptomycin for injection, and may range in severity from mild diarrhea to fatal colitis [see Adverse Reactions (6.2)]. Treatment with antibacterial agents alters the normal flora of the colon, leading to overgrowth of C. difficile.

C. difficile produces toxins A and B, which contribute to the development of CDAD. Hypertoxin-producing strains of C. difficile cause increased morbidity and mortality, since these infections can be refractory to antimicrobial therapy and may require colectomy. CDAD must be considered in all patients who present with diarrhea following antibacterial use. Careful medical history is necessary because CDAD has been reported to occur more than 2 months after the administration of antibacterial agents.

If CDAD is suspected or confirmed, ongoing antibacterial use not directed against C. difficile may need to be discontinued. Appropriate fluid and electrolyte management, protein supplementation, antibacterial treatment of C. difficile, and surgical evaluation should be instituted as clinically indicated.

5.9 Persisting or Relapsing S. aureus Bacteremia/Endocarditis

Patients with persisting or relapsing S. aureus bacteremia/endocarditis or poor clinical response should have repeat blood cultures. If a blood culture is positive for S. aureus, minimum inhibitory concentration (MIC) susceptibility testing of the isolate should be performed using a standardized procedure, and diagnostic evaluation of the patient should be performed to rule out sequestered foci of infection. Appropriate surgical intervention (e.g., debridement, removal of prosthetic devices, valve replacement surgery) and/or consideration of a change in antibacterial regimen may be required.

Failure of treatment due to persisting or relapsing S. aureus bacteremia/endocarditis may be due to reduced daptomycin susceptibility (as evidenced by increasing MIC of the S. aureus isolate) [see Clinical Studies (14.2)].

5.10 Decreased Efficacy in Patients with Moderate Baseline Renal Impairment

Limited data are available from the two Phase 3 complicated skin and skin structure infection (cSSSI) trials regarding clinical efficacy of daptomycin for injection treatment in adult patients with creatinine clearance (CLCR) <50 mL/min; only 31/534 (6%) patients treated with daptomycin for injection in the intent-to-treat (ITT) population had a baseline CLCR <50 mL/min. Table 4 shows the number of adult patients by renal function and treatment group who were clinical successes in the Phase 3 cSSSI trials.

Table 4. Clinical Success Rates by Renal Function and Treatment Group in Phase 3 cSSSI Trials in Adult Patients (Population: ITT)
CLCR | Success Rate n/N (%)
 | Daptomycin for Injection for Injection 4 mg/kg every 24h | Comparator
50-70 mL/min | 25/38 (66%) | 30/48 (63%)
30-<50 mL/min | 7/15 (47%) | 20/35 (57%)

In a subgroup analysis of the ITT population in the Phase 3 S. aureus bacteremia/endocarditis trial, clinical success rates, as determined by a treatment-blinded Adjudication Committee [see Clinical Studies (14.2)], in the daptomycin for injection-treated adult patients were lower in patients with baseline CLCR <50 mL/min (see Table 5). A decrease of the magnitude shown in Table 5 was not observed in comparator-treated patients.

Table 5. Adjudication Committee Clinical Success Rates at Test of Cure by Baseline Creatinine Clearance and Treatment Subgroup in the S. aureus Bacteremia/Endocarditis Trial in Adult Patients (Population: ITT)
 | Success Rate n/N (%)
Baseline CLCR | Daptomycin for Injection 6 mg/kg every 24h |  | Comparator
 | Bacteremia | Right-Sided; Infective Endocarditis | Bacteremia | Right-Sided; Infective Endocarditis
>80 mL/min | 30/50 (60%) | 7/14 (50%) | 19/42 (45%) | 5/11 (46%)
50–80 mL/min | 12/26 (46%) | 1/4 (25%) | 13/31 (42%) | 1/2 (50%)
30–<50 mL/min | 2/14 (14%) | 0/1 (0%) | 7/17 (41%) | 1/1 (100%)

Consider these data when selecting antibacterial therapy for use in adult patients with baseline moderate to severe renal impairment.

5.11 Increased International Normalized Ratio (INR)/Prolonged Prothrombin Time

Clinically relevant plasma concentrations of daptomycin have been observed to cause a significant concentration-dependent false prolongation of prothrombin time (PT) and elevation of International Normalized Ratio (INR) when certain recombinant thromboplastin reagents are utilized for the assay [see Drug Interactions (7.2)].

5.12 Development of Drug-Resistant Bacteria

Prescribing Daptomycin in Sodium Chloride Injection in the absence of a proven or strongly suspected bacterial infection or a prophylactic indication is unlikely to provide benefit to the patient and increases the risk of the development of drug-resistant bacteria.

6 ADVERSE REACTIONS

The following clinically significant adverse reactions are described elsewhere in the labeling:

- Anaphylaxis/Hypersensitivity Reactions [see Warnings and Precautions (5.1)]
- Myopathy and Rhabdomyolysis [see Warnings and Precautions (5.2)]
- Eosinophilic Pneumonia [see Warnings and Precautions (5.3)]
- Drug Reaction with Eosinophilia and Systemic Symptoms [see Warnings and Precautions (5.4)]
- Tubulointerstitial Nephritis [see Warnings and Precautions (5.5)]
- Peripheral Neuropathy [see Warnings and Precautions (5.6)]
- Increased International Normalized Ratio (INR)/Prolonged Prothrombin Time [see Warnings and Precautions (5.11) and Drug Interactions (7.2)]

6.1 Clinical Trials Experience

Because clinical trials are conducted under widely varying conditions, adverse reaction rates observed in the clinical trials of a drug cannot be directly compared to rates in the clinical trials of another drug and may not reflect the rates observed in practice.

Clinical Trial Experience in Adult Patients

Clinical trials enrolled 1,864 adult patients treated with daptomycin for injection and 1,416 treated with comparator.

Complicated Skin and Skin Structure Infection Trials in Adults

In Phase 3 complicated skin and skin structure infection (cSSSI) trials in adult patients, daptomycin for injection was discontinued in 15/534 (2.8%) patients due to an adverse reaction, while comparator was discontinued in 17/558 (3.0%) patients.

The rates of the most common adverse reactions, organized by body system, observed in adult patients with cSSSI (receiving 4 mg/kg daptomycin for injection) are displayed in Table 6.

Table 6. Incidence of Adverse Reactions that Occurred in ≥2% of Adult Patients in the Daptomycin for Injection Treatment Group and ≥ the Comparator Treatment Group in Phase 3 cSSSI Trials
Adverse Reaction | Adult Patients (%)
 | Daptomycin for Injection 4 mg/kg (N=534) | Comparator [Comparator: vancomycin (1 g IV every 12h) or an anti-staphylococcal semi-synthetic penicillin (i.e., nafcillin, oxacillin, cloxacillin, or flucloxacillin; 4 to 12 g/day IV in divided doses).] (N=558)
Gastrointestinal disorders
Diarrhea | 5.2 | 4.3
Nervous system disorders
Headache | 5.4 | 5.4
Dizziness | 2.2 | 2.0
Skin/subcutaneous disorders
Rash | 4.3 | 3.8
Diagnostic investigations
Abnormal liver function tests | 3.0 | 1.6
Elevated CPK | 2.8 | 1.8
Infections
Urinary tract infections | 2.4 | 0.5
Vascular disorders
Hypotension | 2.4 | 1.4
Respiratory disorders
Dyspnea | 2.1 | 1.6

Drug-related adverse reactions (possibly or probably drug-related) that occurred in <1% of adult patients receiving daptomycin for injection in the cSSSI trials are as follows:

Body as a Whole: fatigue, weakness, rigors, flushing, hypersensitivity

Blood/Lymphatic System: leukocytosis, thrombocytopenia, thrombocytosis, eosinophilia, increased International Normalized Ratio (INR)

Cardiovascular System: supraventricular arrhythmia

Dermatologic System: eczema

Digestive System: abdominal distension, stomatitis, jaundice, increased serum lactate dehydrogenase

Metabolic/Nutritional System: hypomagnesemia, increased serum bicarbonate, electrolyte disturbance

Musculoskeletal System: myalgia, muscle cramps, muscle weakness, arthralgia

Nervous System: vertigo, mental status change, paresthesia

Special Senses: taste disturbance, eye irritation

S. aureus Bacteremia/Endocarditis Trial in Adults

In the S. aureus bacteremia/endocarditis trial involving adult patients, daptomycin for injection was discontinued in 20/120 (16.7%) patients due to an adverse reaction, while comparator was discontinued in 21/116 (18.1%) patients.

Serious Gram-negative infections (including bloodstream infections) were reported in 10/120 (8.3%) daptomycin for injection-treated patients and 0/115 comparator-treated patients. Comparator-treated patients received dual therapy that included initial gentamicin for 4 days. Infections were reported during treatment and during early and late follow-up. Gram-negative infections included cholangitis, alcoholic pancreatitis, sternal osteomyelitis/mediastinitis, bowel infarction, recurrent Crohn’s disease, recurrent line sepsis, and recurrent urosepsis caused by a number of different Gram-negative bacteria.

The rates of the most common adverse reactions, organized by System Organ Class (SOC), observed in adult patients with S. aureus bacteremia/endocarditis (receiving 6 mg/kg daptomycin for injection) are displayed in Table 7.

Table 7. Incidence of Adverse Reactions that Occurred in ≥5% of Adult Patients in the Daptomycin for Injection Treatment Group and ≥ the Comparator Treatment Group in the S. aureus Bacteremia/Endocarditis Trial
Adverse Reaction [NOS, not otherwise specified.] | Adult Patients n (%)
 | Daptomycin for Injection 6 mg/kg (N=120) | Comparator [Comparator: vancomycin (1 g IV every 12h) or an anti-staphylococcal semi-synthetic penicillin (i.e., nafcillin, oxacillin, cloxacillin, or flucloxacillin; 2 g IV every 4h), each with initial low-dose gentamicin.] (N=116)
Infections and infestations
Sepsis NOS | 6 (5%) | 3 (3%)
Bacteremia | 6 (5%) | 0 (0%)
Gastrointestinal disorders
Abdominal pain NOS | 7 (6%) | 4 (3%)
General disorders and administration site conditions
Chest pain | 8 (7%) | 7 (6%)
Edema NOS | 8 (7%) | 5 (4%)
Respiratory, thoracic and mediastinal disorders
Pharyngolaryngeal pain | 10 (8%) | 2 (2%)
Skin and subcutaneous tissue disorders
Pruritus | 7 (6%) | 6 (5%)
Sweating increased | 6 (5%) | 0 (0%)
Psychiatric disorders
Insomnia | 11 (9%) | 8 (7%)
Investigations
Blood creatine phosphokinase increased | 8 (7%) | 1 (1%)
Vascular disorders
Hypertension NOS | 7 (6%) | 3 (3%)

The following reactions, not included above, were reported as possibly or probably drug-related in the daptomycin for injection-treated group:

Blood and Lymphatic System Disorders: eosinophilia, lymphadenopathy, thrombocythemia, thrombocytopenia

Cardiac Disorders: atrial fibrillation, atrial flutter, cardiac arrest

Ear and Labyrinth Disorders: tinnitus

Eye Disorders: vision blurred

Gastrointestinal Disorders: dry mouth, epigastric discomfort, gingival pain, hypoesthesia oral

Infections and Infestations: candidal infection NOS, vaginal candidiasis, fungemia, oral candidiasis, urinary tract infection fungal

Investigations: blood phosphorous increased, blood alkaline phosphatase increased, INR increased, liver function test abnormal, alanine aminotransferase increased, aspartate aminotransferase increased, prothrombin time prolonged

Metabolism and Nutrition Disorders: appetite decreased NOS

Musculoskeletal and Connective Tissue Disorders: myalgia

Nervous System Disorders: dyskinesia, paresthesia

Psychiatric Disorders: hallucination NOS

Renal and Urinary Disorders: proteinuria, renal impairment NOS

Skin and Subcutaneous Tissue Disorders: pruritus generalized, rash vesicular

Other Trials in Adults

In Phase 3 trials of community-acquired pneumonia (CAP) in adult patients, the death rate and rates of serious cardiorespiratory adverse events were higher in daptomycin for injection-treated patients than in comparator-treated patients. These differences were due to lack of therapeutic effectiveness of daptomycin for injection in the treatment of CAP in patients experiencing these adverse events [see Indications and Usage (1.4)].

Laboratory Changes in Adults

Complicated Skin and Skin Structure Infection Trials in Adults

In Phase 3 cSSSI trials of adult patients receiving daptomycin for injection at a dose of 4 mg/kg, elevations in CPK were reported as clinical adverse events in 15/534 (2.8%) daptomycin for injection-treated patients, compared with 10/558 (1.8%) comparator-treated patients. Of the 534 patients treated with daptomycin for injection, 1 (0.2%) had symptoms of muscle pain or weakness associated with CPK elevations to greater than 4 times the upper limit of normal (ULN). The symptoms resolved within 3 days and CPK returned to normal within 7 to 10 days after treatment was discontinued [see Warnings and Precautions (5.2)]. Table 8 summarizes the CPK shifts from Baseline through End of Therapy in the cSSSI adult trials.

Table 8. Incidence of CPK Elevations from Baseline during Therapy in Either the Daptomycin for Injection Treatment Group or the Comparator Treatment Group in Phase 3 cSSSI Adult Trials
 | All Adult Patients |  |  |  | Adult Patients with Normal CPK at Baseline
Change in CPK | Daptomycin for Injection 4 mg/kg; (N=430) |  | Comparator [Comparator: vancomycin (1 g IV every 12h) or an anti-staphylococcal semi-synthetic penicillin (i.e., nafcillin, oxacillin, cloxacillin, or flucloxacillin; 4 to 12 g/day IV in divided doses).] (N=459) |  | Daptomycin for Injection 4 mg/kg; (N=374) |  | Comparator (N=392)
 | % | n | % | n | % | n | % | n
No Increase | 90.7 | 390 | 91.1 | 418 | 91.2 | 341 | 91.1 | 357
Maximum Value>1× ULN [ULN (Upper Limit of Normal) is defined as 200 U/L.] | 9.3 | 40 | 8.9 | 41 | 8.8 | 33 | 8.9 | 35
>2× ULN | 4.9 | 21 | 4.8 | 22 | 3.7 | 14 | 3.1 | 12
>4× ULN | 1.4 | 6 | 1.5 | 7 | 1.1 | 4 | 1.0 | 4
>5× ULN | 1.4 | 6 | 0.4 | 2 | 1.1 | 4 | 0.0 | 0
>10× ULN | 0.5 | 2 | 0.2 | 1 | 0.2 | 1 | 0.0 | 0
Note: Elevations in CPK observed in adult patients treated with daptomycin or comparator were not clinically or statistically significantly different.

S. aureus Bacteremia/Endocarditis Trial in Adults

In the S. aureus bacteremia/endocarditis trial in adult patients, at a dose of 6 mg/kg, 11/120 (9.2%) daptomycin for injection-treated patients, including two patients with baseline CPK levels >500 U/L, had CPK elevations to levels >500 U/L, compared with 1/116 (0.9%) comparator-treated patients. Of the 11 daptomycin for injection-treated patients, 4 had prior or concomitant treatment with an HMG-CoA reductase inhibitor. Three of these 11 daptomycin for injection-treated patients discontinued therapy due to CPK elevation, while the one comparator-treated patient did not discontinue therapy [see Warnings and Precautions (5.2)].

Clinical Trial Experience in Pediatric Patients

Complicated Skin and Skin Structure Infection Trial in Pediatric Patients

The safety of daptomycin for injection was evaluated in one clinical trial (in cSSSI), which included 256 pediatric patients (1 to 17 years of age) treated with intravenous daptomycin for injection and 133 patients treated with comparator agents. Patients were given age-dependent doses once daily for a treatment period of up to 14 days (median treatment period was 3 days). The doses given by age group were as follows: 10 mg/kg for 1 to < 2 years, 9 mg/kg for 2 to 6 years, 7 mg/kg for 7 to 11 years and 5 mg/kg for 12 to 17 years of age [see Clinical Studies (14)]. Patients treated with daptomycin for injection were (51%) male, (49%) female and (46%) Caucasian and (32%) Asian.

Adverse Reactions Leading to Discontinuation

In the cSSSI study, daptomycin for injection was discontinued in 7/256 (2.7%) patients due to an adverse reaction, while comparator was discontinued in 7/133 (5.3%) patients.

Most Common Adverse Reactions

The rates of the most common adverse reactions, organized by body system, observed in these pediatric patients with cSSSI are displayed in Table 9.

Table 9. Adverse Reactions that Occurred in ≥2% of Pediatric Patients in the Daptomycin for Injection Treatment-Arm and Greater Than or Equal to the Comparator Treatment-Arm in the cSSSI Pediatric Trial
Adverse Reaction | Daptomycin for Injection (N = 256) | Comparator [Comparators included intravenous therapy with either vancomycin, clindamycin, or an anti-staphylococcal semi-synthetic penicillin (nafcillin, oxacillin or cloxacillin)] (N = 133)
 | n (%) | n (%)
Gastrointestinal disorders
Diarrhea | 18 (7.0) | 7 (5.3)
Vomiting | 7 (2.7) | 1 (0.8)
Abdominal Pain | 5 (2.0) | 0
Skin and subcutaneous tissue disorders
Pruritus | 8 (3.1) | 2 (1.5)
General disorders and administration site conditions
Pyrexia | 10 (3.9) | 4 (3.0)
Investigations
Blood CPK increased | 14 (5.5) | 7 (5.3)
Nervous system disorders
Headache | 7 (2.7) | 3 (2.3)

The safety profile in the clinical trial of cSSSI pediatric patients was similar to that observed in the cSSSI adult patients.

S. aureus Bacteremia Trial in Pediatric Patients

The safety of daptomycin for injection was evaluated in one clinical trial (in S. aureus bacteremia), which treated 55 pediatric patients with intravenous daptomycin for injection and 26 patients with comparator agents. Patients were given age-dependent doses once daily for a treatment period of up to 42 days (mean duration of IV treatment was 12 days). The doses by age group were as follows: 12 mg/kg for 1 to <6 years, 9 mg/kg for 7 to 11 years and 7 mg/kg for 12 to 17 years of age [see Clinical Studies (14)]. Patients treated with daptomycin for injection were (69%) male and (31%) female. No patients 1 to <2 years of age were enrolled.

Adverse Reactions Leading to Discontinuation

In the bacteremia study, daptomycin for injection was discontinued in 3/55 (5.5%) patients due to an adverse reaction, while comparator was discontinued in 2/26 (7.7%) patients.

Most Common Adverse Reactions

The rates of the most common adverse reactions, organized by body system, observed in these pediatric patients with bacteremia are displayed in Table 10.

Table 10. Incidence of Adverse Reactions that Occurred in ≥5% of Pediatric Patients in the Daptomycin for Injection Treatment-Arm and Greater Than or Equal to the Comparator Treatment-Arm in the Pediatric Bacteremia Trial
Adverse Reaction | Daptomycin for Injection (N = 55) | Comparator (N = 26)
 | n (%) | n (%)
Gastrointestinal disorders
Vomiting | 6 (10.9) | 2 (7.7)
Investigations
Blood CPK increased | 4 (7.3) | 0
*Comparators included intravenous therapy with either vancomycin, cefazolin, or an anti-staphylococcal semi-synthetic penicillin (nafcillin, oxacillin or cloxacillin)

6.2 Postmarketing Experience

The following adverse reactions have been identified during postapproval use of daptomycin for injection. Because these reactions are reported voluntarily from a population of uncertain size, it is not always possible to reliably estimate their frequency or establish a causal relationship to drug exposure.

Blood and lymphatic system disorders: anemia, thrombocytopenia

General and administration site conditions: pyrexia

Immune System Disorders: anaphylaxis; hypersensitivity reactions, including angioedema, pruritus, hives, shortness of breath, difficulty swallowing, truncal erythema, and pulmonary eosinophilia [see Contraindications (4) and Warnings and Precautions (5.1)]

Infections and Infestations: Clostridioides difficile–associated diarrhea [see Warnings and Precautions (5.8)]

Laboratory Investigations: platelet count decreased

Musculoskeletal Disorders: myoglobin increased; rhabdomyolysis (some reports involved patients treated concurrently with daptomycin for injection and HMG-CoA reductase inhibitors) [see Warnings and Precautions (5.2), Drug Interactions (7.1), and Clinical Pharmacology (12.3)]

Respiratory, Thoracic, and Mediastinal Disorders: cough, eosinophilic pneumonia, organizing pneumonia [see Warnings and Precautions (5.3)]

Nervous System Disorders: peripheral neuropathy [see Warnings and Precautions (5.6)]

Skin and Subcutaneous Tissue Disorders: serious skin reactions, including drug reaction with eosinophilia and systemic symptoms (DRESS), vesiculobullous rash (with or without mucous membrane involvement, including Stevens-Johnson syndrome [SJS] and toxic epidermal necrolysis [TEN]), and acute generalized exanthematous pustulosis [see Warnings and Precautions (5.4)]

Gastrointestinal Disorders: nausea, vomiting

Metabolic and Nutritional Disorders: hyperkalemia

Renal and urinary disorders: acute kidney injury, renal insufficiency, renal failure, and tubulointerstitial nephritis (TIN) [see Warnings and Precautions (5.5)]

Special Senses: visual disturbances

7 DRUG INTERACTIONS

7.1 HMG-CoA Reductase Inhibitors

In healthy adult subjects, concomitant administration of daptomycin for injection and simvastatin had no effect on plasma trough concentrations of simvastatin, and there were no reports of skeletal myopathy [see Clinical Pharmacology (12.3)].

However, inhibitors of HMG-CoA reductase may cause myopathy, which is manifested as muscle pain or weakness associated with elevated levels of creatine phosphokinase (CPK). In the adult Phase 3 S. aureus bacteremia/endocarditis trial, some patients who received prior or concomitant treatment with an HMG-CoA reductase inhibitor developed elevated CPK [see Adverse Reactions (6.1)]. Experience with the coadministration of HMG-CoA reductase inhibitors and daptomycin for injection in patients is limited; therefore, consideration should be given to suspending use of HMG-CoA reductase inhibitors temporarily in patients receiving Daptomycin in Sodium Chloride Injection.

7.2 Drug-Laboratory Test Interactions

Clinically relevant plasma concentrations of daptomycin have been observed to cause a significant concentration-dependent false prolongation of prothrombin time (PT) and elevation of International Normalized Ratio (INR) when certain recombinant thromboplastin reagents are utilized for the assay. The possibility of an erroneously elevated PT/INR result due to interaction with a recombinant thromboplastin reagent may be minimized by drawing specimens for PT or INR testing near the time of trough plasma concentrations of daptomycin. However, sufficient daptomycin concentrations may be present at trough to cause interaction.

If confronted with an abnormally high PT/INR result in a patient being treated with Daptomycin in Sodium Chloride Injection, it is recommended that clinicians:

1. Repeat the assessment of PT/INR, requesting that the specimen be drawn just prior to the next Daptomycin in Sodium Chloride Injection dose (i.e., at trough concentration). If the PT/INR value obtained at trough remains substantially elevated above what would otherwise be expected, consider evaluating PT/INR utilizing an alternative method.
2. Evaluate for other causes of abnormally elevated PT/INR results.

8 USE IN SPECIFIC POPULATIONS

8.1 Pregnancy

Risk Summary

Limited published data on use of daptomycin for injection in pregnant women are insufficient to inform a drug-associated risk for major birth defects and miscarriage. In animal reproduction studies performed in rats and rabbits daptomycin was administered intravenously during organogenesis at doses 2 and 4–times, respectively, the recommended 6 mg/kg human dose (on a body surface area basis). No evidence of adverse developmental outcomes was observed.

The background risk of major birth defects and miscarriage for the indicated population is unknown. All pregnancies have a background risk of birth defect, loss, or other adverse outcomes. In the U.S. general population, the estimated background risk of major birth defects and miscarriage in clinically recognized pregnancies is 2-4% and 15-20%, respectively.

Data

Animal Data

In pregnant rats, daptomycin was administered intravenously at doses of 5, 20, or 75 mg/kg/day during the gestation days 6 to 18. Maternal body weight gain was decreased at 75 mg/kg/day. No embryo/fetal effects were noted at the highest dose of 75 mg/kg/day, a dose approximately 2-fold higher than in humans at the recommended maximum dose of 6 mg/kg (based on body surface area).

In pregnant rabbits, daptomycin was administered intravenously at doses of 5, 20, or 75 mg/kg/day during the gestation days 6 to 15. Maternal body weight gain and food consumption were decreased at 75 mg/kg/day. No embryo/fetal effects were noted at the highest dose of 75 mg/kg/day, a dose approximately 4-fold higher than in humans at the maximum recommended dose of 6 mg/kg (based on body surface area).

In a combined fertility and pre/postnatal development study, daptomycin was administered intravenously to female rats at doses of 2, 25, 75 mg/kg/day from 14-days pre-mating through lactation/postpartum day 20). No effects on pre/postnatal development were observed up to the highest dose of 75 mg/kg/day, a dose approximately 2-fold higher than the maximum recommended human dose of 6 mg/kg (based on body surface area)^1.

8.2 Lactation

Risk Summary

Limited published data report that daptomycin is present in human milk at infant doses of 0.1% of the maternal dose (see Data)^2,3,4. There is no information on the effects of daptomycin on the breastfed infant or the effects of daptomycin on milk production. The developmental and health benefits of breastfeeding should be considered along with the mother’s clinical need for daptomycin for injection and any potential adverse effects on the breastfed infant from daptomycin for injection or from the underlying maternal condition.

8.4 Pediatric Use

The safety and effectiveness of daptomycin for injection in the treatment of cSSSI and S. aureus bloodstream infections (bacteremia) have been established in the age groups 1 to 17 years of age. Use of daptomycin for injection in these age groups is supported by evidence from adequate and well-controlled studies in adults, with additional data from pharmacokinetic studies in pediatric patients, and from safety, efficacy and PK studies in pediatric patients with cSSSI and S. aureus bloodstream infections [see Adverse Reactions (6.1), Clinical Pharmacology (12.3), and Clinical Studies (14.1, 14.2)].

Safety and effectiveness in pediatric patients below the age of one year have not been established. Avoid use of Daptomycin in Sodium Chloride Injection in pediatric patients younger than one year of age due to the risk of potential effects on muscular, neuromuscular, and/or nervous systems (either peripheral and/or central) observed in neonatal dogs [see Warnings and Precautions (5.7) and Nonclinical Toxicology (13.2)].

Because of the limitations of the available strengths and administration requirements (i.e., administration of fractional doses is not recommended) of Daptomycin in Sodium Chloride Injection, and to avoid unintentional overdose, this product is not recommended for use if a dose of Daptomycin in Sodium Chloride Injection is required that does not equal 350 mg, 500 mg, 700 mg or 1,000 mg and an alternative formulation of daptomycin should be considered [see Dosage and Administration (2.3, 2.5)].

Daptomycin in Sodium Chloride Injection is not indicated in pediatric patients with renal impairment because dosage has not been established in these patients.

Daptomycin in Sodium Chloride Injection has not been studied in pediatric patients with other bacterial infections.

8.5 Geriatric Use

Of the 534 adult patients treated with daptomycin for injection in Phase 3 controlled clinical trials of complicated skin and skin structure infections (cSSSI), 27% were 65 years of age or older and 12% were 75 years of age or older. Of the 120 adult patients treated with daptomycin for injection in the Phase 3 controlled clinical trial of S. aureus bacteremia/endocarditis, 25% were 65 years of age or older and 16% were 75 years of age or older. In Phase 3 adult clinical trials of cSSSI and S. aureus bacteremia/endocarditis, clinical success rates were lower in patients ≥65 years of age than in patients <65 years of age. In addition, treatment-emergent adverse events were more common in patients ≥65 years of age than in patients <65 years of age.

The exposure of daptomycin was higher in healthy elderly subjects than in healthy young adult subjects. However, no adjustment of Daptomycin in Sodium Chloride Injection dosage is warranted for elderly patients with creatinine clearance (CLCR) ≥30 mL/min [see Dosage and Administration (2.6) and Clinical Pharmacology (12.3)].

8.6 Patients with Renal Impairment

Daptomycin is eliminated primarily by the kidneys; therefore, a modification of Daptomycin in Sodium Chloride Injection dosage interval is recommended for adult patients with CLCR <30 mL/min, including patients receiving hemodialysis or continuous ambulatory peritoneal dialysis (CAPD). In adult patients with renal impairment, both renal function and creatine phosphokinase (CPK) should be monitored more frequently than once weekly [see Dosage and Administration (2.6), Warnings and Precautions (5.2, 5.10), and Clinical Pharmacology (12.3)].

The dosage regimen for Daptomycin in Sodium Chloride Injection in pediatric patients with renal impairment has not been established.

10 OVERDOSAGE

In the event of overdosage, supportive care is advised with maintenance of glomerular filtration. Daptomycin is cleared slowly from the body by hemodialysis (approximately 15% of the administered dose is removed over 4 hours) and by peritoneal dialysis (approximately 11% of the administered dose is removed over 48 hours). The use of high-flux dialysis membranes during 4 hours of hemodialysis may increase the percentage of dose removed compared with that removed by low-flux membranes.

11 DESCRIPTION

Daptomycin in Sodium Chloride Injection contains daptomycin, a cyclic lipopeptide antibacterial agent derived from the fermentation of Streptomyces roseosporus. The chemical name is N-decanoyl-L-tryptophyl-D-asparaginyl-L-aspartyl-L-threonylglycyl-L-ornithyl-L-aspartyl-D-alanyl-L-aspartylglycyl-D-seryl-threo-3-methyl-L-glutamyl-3-anthraniloyl-L-alanine ℇ1-lactone. The chemical structure is:

The empirical formula is C72H101N17O26; the molecular weight is 1620.67.

Daptomycin in Sodium Chloride Injection is a single-dose frozen, premixed, iso-osmotic, sterile, nonpyrogenic solution containing either 350 milligrams or 500 milligrams of daptomycin, per 50 mL GALAXY container (PL 2040 Plastic); or 700 milligrams or 1,000 milligrams daptomycin, per 100 mL GALAXY container (PL 2040 Plastic). Daptomycin in Sodium Chloride Injection must be a clear, slightly yellow solution. Sodium Chloride, USP (0.9%) has been added to adjust osmolality. The approximate osmolality is 320 mOsmol/kg. Monobasic Sodium Phosphate, USP and Dibasic Sodium Phosphate, USP were added as buffer agents and the pH may have been adjusted with Hydrochloric Acid, NF and/or Sodium Hydroxide, NF. Water for Injection, USP is added as drug vehicle. Contains no preservative. The solution is intended for intravenous use after thawing to room temperature.

This GALAXY container (PL 2040 Plastic) is fabricated from a specially designed multilayer plastic (PL 2040). Solutions are in contact with the polyethylene layer of this container and can leach out certain chemical components of the plastic in very small amounts within the expiration period. However, the suitability of the plastic has been confirmed in tests in animals according to the USP biological tests for plastic containers, as well as by tissue culture toxicity studies.

12 CLINICAL PHARMACOLOGY

12.1 Mechanism of Action

Daptomycin is an antibacterial drug [see Clinical Pharmacology (12.4)].

12.2 Pharmacodynamics

Based on animal models of infection, the antimicrobial activity of daptomycin appears to correlate with the AUC/MIC (area under the concentration-time curve/minimum inhibitory concentration) ratio for certain pathogens, including S. aureus. The principal pharmacokinetic/pharmacodynamic parameter best associated with clinical and microbiological cure has not been elucidated in clinical trials with daptomycin for injection.

12.3 Pharmacokinetics

Daptomycin for Injection Administered over a 30-Minute Period in Adults

The mean and standard deviation (SD) pharmacokinetic parameters of daptomycin at steady-state following intravenous (IV) administration of daptomycin for injection over a 30-minute period at 4 to 12 mg/kg every 24h to healthy young adults are summarized in Table 11.

Table 11. Mean (SD) Daptomycin Pharmacokinetic Parameters in Healthy Adult Volunteers at Steady-State
Dose [Daptomycin was administered by IV infusion over a 30-minute period.] [Doses of Daptomycin in excess of 6 mg/kg have not been approved.] (mg/kg) | Pharmacokinetic Parameters [AUC0-24, area under the concentration-time curve from 0 to 24 hours; t1/2, elimination half-life; Vss, volume of distribution at steady-state; CLT, total plasma clearance; Cmax, maximum plasma concentration.]
 | AUC0-24 (mcg•h/mL) | t1/2 (h) | Vss (L/kg) | CLT (mL/h/kg) | Cmax (mcg/mL)
4 (N=6) | 494 (75) | 8.1 (1.0) | 0.096 (0.009) | 8.3 (1.3) | 57.8 (3.0)
6 (N=6) | 632 (78) | 7.9 (1.0) | 0.101 (0.007) | 9.1 (1.5) | 93.9 (6.0)
8 (N=6) | 858 (213) | 8.3 (2.2) | 0.101 (0.013) | 9.0 (3.0) | 123.3 (16.0)
10 (N=9) | 1039 (178) | 7.9 (0.6) | 0.098 (0.017) | 8.8 (2.2) | 141.1 (24.0)
12 (N=9) | 1277 (253) | 7.7 (1.1) | 0.097 (0.018) | 9.0 (2.8) | 183.7 (25.0)

Daptomycin pharmacokinetics were generally linear and time-independent at daptomycin for injection doses of 4 to 12 mg/kg every 24h administered by IV infusion over a 30-minute period for up to 14 days. Steady-state trough concentrations were achieved by the third daily dose. The mean (SD) steady-state trough concentrations attained following the administration of 4, 6, 8, 10, and 12 mg/kg every 24h were 5.9 (1.6), 6.7 (1.6), 10.3 (5.5), 12.9 (2.9), and 13.7 (5.2) mcg/mL, respectively.

Distribution

Daptomycin is reversibly bound to human plasma proteins, primarily to serum albumin, in a concentration-independent manner. The overall mean binding ranges from 90 to 93%.

In clinical studies, mean serum protein binding in adult subjects with creatinine clearance (CLCR) ≥30 mL/min was comparable to that observed in healthy adult subjects with normal renal function. However, there was a trend toward decreasing serum protein binding among subjects with CLCR <30 mL/min (88%), including those receiving hemodialysis (86%) and continuous ambulatory peritoneal dialysis (CAPD) (84%). The protein binding of daptomycin in adult subjects with moderate hepatic impairment (Child-Pugh Class B) was similar to that in healthy adult subjects.

The volume of distribution at steady-state (Vss) of daptomycin in healthy adult subjects was approximately 0.1 L/kg and was independent of dose.

Elimination

Metabolism
In in vitro studies, daptomycin was not metabolized by human liver microsomes.
In 5 healthy adults after infusion of radiolabeled ^14C-daptomycin, the plasma total radioactivity was similar to the concentration determined by microbiological assay. Inactive metabolites were detected in urine, as determined by the difference between total radioactive concentrations and microbiologically active concentrations. In a separate study, no metabolites were observed in plasma on Day 1 following the administration of daptomycin for injection at 6 mg/kg to adult subjects. Minor amounts of three oxidative metabolites and one unidentified compound were detected in urine. The site of metabolism has not been identified.
Excretion
Daptomycin is excreted primarily by the kidneys. In a mass balance study of 5 healthy adult subjects using radiolabeled daptomycin, approximately 78% of the administered dose was recovered from urine based on total radioactivity (approximately 52% of the dose based on microbiologically active concentrations), and 5.7% of the administered dose was recovered from feces (collected for up to 9 days) based on total radioactivity.

Specific Populations

Patients with Renal Impairment

Population-derived pharmacokinetic parameters were determined for infected adult patients (complicated skin and skin structure infections [cSSSI] and S. aureus bacteremia) and noninfected adult subjects with various degrees of renal function (Table 12). Total plasma clearance (CLT), elimination half-life (t1/2), and volume of distribution at steady-state (Vss) in patients with cSSSI were similar to those in patients with S. aureus bacteremia. Following administration of daptomycin for injection 4 mg/kg every 24h by IV infusion over a 30-minute period, the mean CLT was 9%, 22%, and 46% lower among subjects and patients with mild (CLCR 50–80 mL/min), moderate (CLCR 30–<50 mL/min), and severe (CLCR <30 mL/min) renal impairment, respectively, than in those with normal renal function (CLCR >80 mL/min). The mean steady-state systemic exposure (AUC), t1/2, and Vss increased with decreasing renal function, although the mean AUC for patients with CLCR 30–80 mL/min was not markedly different from the mean AUC for patients with normal renal function. The mean AUC for patients with CLCR <30 mL/min and for patients on dialysis (CAPD and hemodialysis dosed post-dialysis) was approximately 2 and 3 times higher, respectively, than for patients with normal renal function. The mean Cmax ranged from 60 to 70 mcg/mL in patients with CLCR ≥30 mL/min, while the mean Cmax for patients with CLCR <30 mL/min ranged from 41 to 58 mcg/mL. After administration of daptomycin for injection 6 mg/kg every 24h by IV infusion over a 30-minute period, the mean Cmax ranged from 80 to 114 mcg/mL in patients with mild to moderate renal impairment and was similar to that of patients with normal renal function.

Table 12. Mean (SD) Daptomycin Population Pharmacokinetic Parameters Following Infusion of Daptomycin for Injection 4 mg/kg or 6 mg/kg to Infected Adult Patients and Noninfected Adult Subjects with Various Degrees of Renal Function
Renal Function | Pharmacokinetic Parameters [CLCR, creatinine clearance estimated using the Cockcroft-Gault equation with actual body weight; CAPD, continuous ambulatory peritoneal dialysis; AUC0-∞, area under the concentration-time curve extrapolated to infinity; AUCss, area under the concentration-time curve calculated over the 24-hour dosing interval at steady-state; Cmin,ss, trough concentration at steady-state; NA, not applicable.]
 | t1/2 [Parameters obtained following a single dose from patients with complicated skin and skin structure infections and healthy subjects.]; (h); 4 mg/kg | Vss; (L/kg); 4 mg/kg | CLT; (mL/h/kg); 4 mg/kg | AUC0-∞; (mcg•h/mL); 4 mg/kg | AUCss [Parameters obtained at steady-state from patients with S. aureus bacteremia.]; (mcg•h/mL); 6 mg/kg | Cmin,ss; (mcg/mL); 6 mg/kg
Normal; (CLCR >80 mL/min) | 9.39 (4.74); N=165 | 0.13 (0.05); N=165 | 10.9 (4.0); N=165 | 417 (155); N=165 | 545 (296); N=62 | 6.9 (3.5); N=61
Mild Renal; Impairment; (CLCR 50– 80 mL/min) | 10.75 (8.36); N=64 | 0.12 (0.05); N=64 | 9.9 (4.0); N=64 | 466 (177); N=64 | 637 (215); N=29 | 12.4 (5.6); N=29
Moderate Renal; Impairment; (CLCR 30– <50 mL/min) | 14.70 (10.50); N=24 | 0.15 (0.06); N=24 | 8.5 (3.4); N=24 | 560 (258); N=24 | 868 (349); N=15 | 19.0 (9.0); N=14
Severe Renal Impairment; (CLCR <30 mL/min) | 27.83 (14.85); N=8 | 0.20 (0.15); N=8 | 5.9 (3.9); N=8 | 925 (467); N=8 | 1050 (892); N=2 | 24.4; (21.4); N=2
Hemodialysis | 30.51 (6.51); N=16 | 0.16 (0.04); N=16 | 3.9 (2.1); N=16 | 1193 (399); N=16 | NA | NA
CAPD | 27.56 (4.53); N=5 | 0.11 (0.02); N=5 | 2.9 (0.4); N=5 | 1409 (238); N=5 | NA | NA
Note: Daptomycin was administered over a 30-minute period.

Because renal excretion is the primary route of elimination, adjustment of Daptomycin in Sodium Chloride Injection dosage interval is necessary in adult patients with severe renal impairment (CLCR <30 mL/min) [see Dosage and Administration (2.6)].

Patients with Hepatic Impairment

The pharmacokinetics of daptomycin were evaluated in 10 adult subjects with moderate hepatic impairment (Child-Pugh Class B) and compared with those in healthy adult volunteers (N=9) matched for gender, age, and weight. The pharmacokinetics of daptomycin were not altered in subjects with moderate hepatic impairment. No dosage adjustment is warranted when Daptomycin in Sodium Chloride Injection is administered to patients with mild to moderate hepatic impairment. The pharmacokinetics of daptomycin in patients with severe hepatic impairment (Child-Pugh Class C) have not been evaluated.

Gender

No clinically significant gender-related differences in daptomycin pharmacokinetics have been observed. No dosage adjustment is warranted based on gender when Daptomycin in Sodium Chloride Injection is administered.

Geriatric Patients

The pharmacokinetics of daptomycin were evaluated in 12 healthy elderly subjects (≥75 years of age) and 11 healthy young adult controls (18 to 30 years of age). Following administration of a single 4 mg/kg dose of daptomycin for injection by IV infusion over a 30-minute period, the mean total clearance of daptomycin was approximately 35% lower and the mean AUC0-∞ was approximately 58% higher in elderly subjects than in healthy young adult subjects. There were no differences in Cmax [see Use in Specific Populations (8.5)].

Obese Patients

The pharmacokinetics of daptomycin were evaluated in 6 moderately obese (Body Mass Index [BMI] 25 to 39.9 kg/m^2) and 6 extremely obese (BMI ≥40 kg/m^2) adult subjects and controls matched for age, gender, and renal function. Following administration of daptomycin for injection by IV infusion over a 30-minute period as a single 4 mg/kg dose based on total body weight, the total plasma clearance of daptomycin normalized to total body weight was approximately 15% lower in moderately obese subjects and 23% lower in extremely obese subjects than in nonobese controls. The AUC0-∞ of daptomycin was approximately 30% higher in moderately obese subjects and 31% higher in extremely obese subjects than in nonobese controls. The differences were most likely due to differences in the renal clearance of daptomycin. No adjustment of Daptomycin in Sodium Chloride Injection dosage is warranted in obese patients.

Pediatric Patients

The pharmacokinetics of daptomycin in pediatric subjects was evaluated in 3 single-dose pharmacokinetic studies. In general, body weight-normalized total body clearance in pediatric patients was higher than in adults and increased with a decrease of age, whereas elimination half-life tends to decrease with a decrease of age. Body weight-normalized total body clearance and elimination half-life of daptomycin in children 2 to 6 years of age were similar at different doses.
A study was conducted to assess safety, efficacy, and pharmacokinetics of daptomycin in pediatric patients (1 to 17 years old, inclusive) with cSSSI caused by Gram-positive pathogens. Patients were enrolled into 4 age groups [see Clinical Studies (14.1)], and intravenous daptomycin for injection doses of 5 to 10 mg/kg once daily were administered. Following administration of multiple doses, daptomycin exposure (AUCss and Cmax,ss) was similar across different age groups after dose adjustment based on body weight and age (Table 13).

Table 13. Mean (SD) Daptomycin Population Pharmacokinetic Parameters in cSSSI Pediatric Patients
Age | Pharmacokinetic Parameters
 | Dose (mg/kg) | Infusion; Duration; (min) | AUCss (mcg•h/mL) | t1/2; (h) | Vss (mL) | CLT (mL/h/kg) | Cmax,ss; (mcg/mL)
12 to 17 years; (N=6) | 5 | 30 | 434; (67.9) | 7.1; (0.9) | 8200; (3250) | 11.8; (2.15) | 76.4 (6.75)
7 to 11 years; (N=2) | 7 | 30 | 543 [Mean is calculated from N=2] | 6.8 | 4470 | 13.2 | 92.4
2 to 6 years; (N=7) | 9 | 60 | 452; (93.1) | 4.6; (0.8) | 2750; (832) | 20.8; (4.29) | 90.3 (14.0)
1 to less than 2 years; (N=27) | 10 | 60 | 462; (138) | 4.8; (0.6) | 1670; (446) | 23.1; (5.43) | 81.6 (20.7)
AUCss, area under the concentration-time curve at steady state; CLT, clearance normalized to body weight;
Vss, volume of distribution at steady state; t½, terminal half-life

A study was conducted to assess safety, efficacy, and pharmacokinetics of daptomycin in pediatric patients with S. aureus bacteremia. Patients were enrolled into 3 age groups [see Clinical Studies (14.2)], and intravenous doses of 7 to 12 mg/kg once daily were administered. Following administration of multiple doses, daptomycin exposure (AUCss and Cmax,ss) was similar across different age groups after dose adjustment based on body weight and age (Table 14).

Table 14. Mean (SD) of Daptomycin Pharmacokinetics in Bacteremia Pediatric Patients
 | Pharmacokinetic Parameters
Age | Dose (mg/kg) | Infusion; Duration; (min) | AUCss (mcg•h/mL) | t1/2 (h) | Vss (mL) | CLT (mL/h/kg) | Cmax,ss; (mcg/mL)
12 to 17 years; (N=13) | 7 | 30 | 656; (334) | 7.5; (2.3) | 6420; (1980) | 12.4; (3.9) | 104; (35.5)
7 to 11 years; (N=19) | 9 | 30 | 579; (116) | 6.0; (0.8) | 4510; (1470) | 15.9; (2.8) | 104; (14.5)
2 to 6 years; (N=19) | 12 | 60 | 620; (109) | 5.1; (0.6) | 2200; (570) | 19.9; (3.4) | 106; (12.8)
AUCss, area under the concentration-time curve at steady state; CLT, clearance normalized to body weight; Vss, volume of distribution at steady state; t½, terminal half-life
No patients 1 to <2 years of age were enrolled in the study. Simulation using a population pharmacokinetic model demonstrated that the AUCss of daptomycin in pediatric patients 1 to <2 years of age receiving 12 mg/kg once daily would be comparable to that in adult patients receiving 6 mg/kg once daily.

Drug Interaction Studies

In Vitro Studies

In vitro studies with human hepatocytes indicate that daptomycin does not inhibit or induce the activities of the following human cytochrome P450 isoforms: 1A2, 2A6, 2C9, 2C19, 2D6, 2E1, and 3A4. It is unlikely that daptomycin will inhibit or induce the metabolism of drugs metabolized by the P450 system.

Aztreonam

In a study in which 15 healthy adult subjects received a single dose of daptomycin for injection 6 mg/kg IV and a combination dose of daptomycin for injection 6 mg/kg IV and aztreonam 1 g IV, administered over a 30-minute period, the Cmax and AUC0-∞ of daptomycin were not significantly altered by aztreonam.

Tobramycin

In a study in which 6 healthy adult males received a single dose of daptomycin for injection 2 mg/kg IV, tobramycin 1 mg/kg IV, and both in combination, administered over a 30-minute period, the mean Cmax and AUC0-∞ of daptomycin were 12.7% and 8.7% higher, respectively, when daptomycin for injection was coadministered with tobramycin. The mean Cmax and AUC0-∞ of tobramycin were 10.7% and 6.6% lower, respectively, when tobramycin was coadministered with daptomycin for injection. These differences were not statistically significant. The interaction between daptomycin and tobramycin with a clinical dose of Daptomycin in Sodium Chloride Injection is unknown.

Warfarin

In 16 healthy adult subjects, administration of daptomycin for injection 6 mg/kg every 24h by IV infusion over a 30-minute period for 5 days, with coadministration of a single oral dose of warfarin (25 mg) on the 5th day, had no significant effect on the pharmacokinetics of either drug and did not significantly alter the INR (International Normalized Ratio).

Simvastatin

In 20 healthy adult subjects on a stable daily dose of simvastatin 40 mg, administration of daptomycin for injection 4 mg/kg every 24h by IV infusion over a 30-minute period for 14 days (N=10) had no effect on plasma trough concentrations of simvastatin and was not associated with a higher incidence of adverse events, including skeletal myopathy, than in subjects receiving placebo once daily (N=10) [see Warnings and Precautions (5.2) and Drug Interactions (7.1)].

Probenecid

Concomitant administration of probenecid (500 mg 4 times daily) and a single dose of daptomycin for injection 4 mg/kg by IV infusion over a 30-minute period in adults did not significantly alter the Cmax or AUC0-∞ of daptomycin.

12.4 Microbiology

Daptomycin belongs to the cyclic lipopeptide class of antibacterials. Daptomycin has clinical utility in the treatment of infections caused by aerobic, Gram-positive bacteria. The in vitro spectrum of activity of daptomycin encompasses most clinically relevant Gram-positive pathogenic bacteria.

Daptomycin exhibits rapid, concentration-dependent bactericidal activity against Gram-positive bacteria in vitro. This has been demonstrated both by time-kill curves and by MBC/MIC (minimum bactericidal concentration/minimum inhibitory concentration) ratios using broth dilution methodology. Daptomycin maintained bactericidal activity in vitro against stationary phase S. aureus in simulated endocardial vegetations. The clinical significance of this is not known.

Mechanism of Action

Daptomycin binds to bacterial cell membranes and causes a rapid depolarization of membrane potential. This loss of membrane potential causes inhibition of DNA, RNA, and protein synthesis, which results in bacterial cell death.

Resistance

The mechanism(s) of daptomycin resistance is not fully understood. Currently, there are no known transferable elements that confer resistance to daptomycin.

Interactions with Other Antibacterials

In vitro studies have investigated daptomycin interactions with other antibacterials. Antagonism, as determined by kill curve studies, has not been observed. In vitro synergistic interactions of daptomycin with aminoglycosides, β-lactam antibacterials, and rifampin have been shown against some isolates of staphylococci (including some methicillin-resistant isolates) and enterococci (including some vancomycin-resistant isolates).

Complicated Skin and Skin Structure Infection (cSSSI) Trials in Adults

The emergence of daptomycin non-susceptible isolates occurred in 2 infected patients across the set of Phase 2 and pivotal Phase 3 clinical trials of cSSSI in adult patients. In one case, a non-susceptible S. aureus was isolated from a patient in a Phase 2 trial who received daptomycin for injection at less than the protocol-specified dose for the initial 5 days of therapy. In the second case, a non-susceptible Enterococcus faecalis was isolated from a patient with an infected chronic decubitus ulcer who was enrolled in a salvage trial.

S. aureus Bacteremia/Endocarditis and Other Post-Approval Trials in Adults

In subsequent clinical trials in adult patients, non-susceptible isolates were recovered. S. aureus was isolated from a patient in a compassionate-use trial and from 7 patients in the S. aureus bacteremia/endocarditis trial [see Clinical Studies (14.2)]. An E. faecium was isolated from a patient in a vancomycin-resistant enterococci trial.

Antimicrobial Activity

Daptomycin has been shown to be active against most isolates of the following microorganisms both in vitro and in clinical infections [see Indications and Usage (1)].

Gram-Positive Bacteria
Enterococcus faecalis (vancomycin-susceptible isolates only)
Staphylococcus aureus (including methicillin-resistant isolates)
Streptococcus agalactiae
Streptococcus dysgalactiae subsp. equisimilis
Streptococcus pyogenes

The following in vitro data are available, but their clinical significance is unknown. At least 90 percent of the following bacteria exhibit an in vitro minimum inhibitory concentration (MIC) less than or equal to the susceptible breakpoint for daptomycin against isolates of similar genus or organism group. However, the efficacy of daptomycin in treating clinical infections caused by these bacteria has not been established in adequate and well-controlled clinical trials.

Gram-Positive Bacteria
Corynebacterium jeikeium
Enterococcus faecalis (vancomycin-resistant isolates)
Enterococcus faecium (including vancomycin-resistant isolates) Staphylococcus epidermidis (including methicillin-resistant isolates)
Staphylococcus haemolyticus

Susceptibility Testing

For specific information regarding susceptibility test interpretive criteria and associated test methods and quality control standards recognized by FDA for daptomycin, please see: https://www.fda.gov/STIC.

13 NONCLINICAL TOXICOLOGY

13.1 Carcinogenesis, Mutagenesis, Impairment of Fertility

Long-term carcinogenicity studies in animals have not been conducted to evaluate the carcinogenic potential of daptomycin for injection. However, neither mutagenic nor clastogenic potential was found in a battery of genotoxicity tests, including the Ames assay, a mammalian cell gene mutation assay, a test for chromosomal aberrations in Chinese hamster ovary cells, an in vivo micronucleus assay, an in vitro DNA repair assay, and an in vivo sister chromatid exchange assay in Chinese hamsters.

Daptomycin did not affect the fertility or reproductive performance of male and female rats when administered intravenously at doses of 25, 75, or 150 mg/kg/day, which is approximately up to 9 times the estimated human exposure level based upon AUCs (or approximately up to 4 times the recommended human dose of 6 mg/kg based on body surface area comparison).

13.2 Animal Toxicology and/or Pharmacology

Adult Animals

In animals, daptomycin administration has been associated with effects on skeletal muscle. However, there were no changes in cardiac or smooth muscle. Skeletal muscle effects were characterized by microscopic degenerative/regenerative changes and variable elevations in creatine phosphokinase (CPK). No fibrosis or rhabdomyolysis was evident in repeat-dose studies up to the highest doses tested in rats (150 mg/kg/day) and dogs (100 mg/kg/day). The degree of skeletal myopathy showed no increase when treatment was extended from 1 month to up to 6 months. Severity was dose-dependent. All muscle effects, including microscopic changes, were fully reversible within 30 days following the cessation of dosing.

In adult animals, effects on peripheral nerve (characterized by axonal degeneration and frequently accompanied by significant losses of patellar reflex, gag reflex, and pain perception) were observed at daptomycin doses higher than those associated with skeletal myopathy. Deficits in the dogs’ patellar reflexes were seen within 2 weeks after the start of treatment at 40 mg/kg/day (9 times the human Cmax at the 6 mg/kg/day dose), with some clinical improvement noted within 2 weeks after the cessation of dosing. However, at 75 mg/kg/day for 1 month, 7 of 8 dogs failed to regain full patellar reflex responses within a 3-month recovery period. In a separate study in dogs receiving doses of 75 and 100 mg/kg/day for 2 weeks, minimal residual histological changes were noted at 6 months after the cessation of dosing. However, recovery of peripheral nerve function was evident.

Tissue distribution studies in rats showed that daptomycin is retained in the kidney but appears to penetrate the blood-brain barrier only minimally following single and multiple doses.

Juvenile Animals

Target organs of daptomycin-related effects in 7-week-old juvenile dogs were skeletal muscle and nerve, the same target organs as in adult dogs. In juvenile dogs, nerve effects were noted at lower daptomycin blood concentrations than in adult dogs following 28 days of dosing. In contrast to adult dogs, juvenile dogs also showed evidence of effects in nerves of the spinal cord as well as peripheral nerves after 28 days of dosing. No nerve effects were noted in juvenile dogs following 14 days of dosing at doses up to 75 mg/kg/day.

Administration of daptomycin to 7-week-old juvenile dogs for 28 days at doses of 50 mg/kg/day produced minimal degenerative effects on the peripheral nerve and spinal cord in several animals, with no corresponding clinical signs. A dose of 150 mg/kg/day for 28 days produced minimal degeneration in the peripheral nerve and spinal cord as well as minimal to mild degeneration of the skeletal muscle in a majority of animals, accompanied by slight to severe muscle weakness evident in most dogs. Following a 28-day recovery phase, microscopic examination revealed recovery of the skeletal muscle and the ulnar nerve effects, but nerve degeneration in the sciatic nerve and spinal cord was still observed in all 150 mg/kg/day dogs.

Following once-daily administration of daptomycin to juvenile dogs for 28 days, microscopic effects in nerve tissue were noted at a Cmax value of 417 mcg/mL, which is approximately 3-fold less than the Cmax value associated with nerve effects in adult dogs treated once daily with daptomycin for 28 days (1308 mcg/mL).

Neonatal Animals

Neonatal dogs (4 to 31 days old) were more sensitive to daptomycin-related adverse nervous system and/or muscular system effects than either juvenile or adult dogs. In neonatal dogs, adverse nervous system and/or muscular system effects were associated with a Cmax value approximately 3-fold less than the Cmax in juvenile dogs, and 9-fold less than the Cmax in adult dogs following 28 days of dosing. At a dose of 25 mg/kg/day with associated Cmax and AUCinf values of 147 mcg/mL and 717 mcg•h/mL, respectively (1.6 and 1.0-fold the adult human Cmax and AUC, respectively, at the 6 mg/kg/day dose), mild clinical signs of twitching and one incidence of muscle rigidity were observed with no corresponding effect on body weight. These effects were found to be reversible within 28 days after treatment had stopped.

At higher dose levels of 50 and 75 mg/kg/day with associated Cmax and AUCinf values of ≥321 mcg/mL and ≥1470 mcg•h/mL, respectively, marked clinical signs of twitching, muscle rigidity in the limbs, and impaired use of limbs were observed. Resulting decreases in body weights and overall body condition at doses ≥50 mg/kg/day necessitated early discontinuation by postnatal day (PND) 19.

Histopathological assessment did not reveal any daptomycin-related changes in the peripheral and central nervous system tissue, as well as in the skeletal muscle or other tissues assessed, at any dose level.

No adverse effects were observed in the dogs that received daptomycin at 10 mg/kg/day, the NOAEL, with associated Cmax and AUCinf values of 62 mcg/mL and 247 mcg•h/mL, respectively (or 0.6 and 0.4-fold the adult human Cmax and AUC, respectively at the 6 mg/kg dose).

14 CLINICAL STUDIES

14.1 Complicated Skin and Skin Structure Infections

Adults with cSSSI

Adult patients with clinically documented complicated skin and skin structure infections (cSSSI) (Table 15) were enrolled in two randomized, multinational, multicenter, investigator-blinded trials comparing daptomycin for injection (4 mg/kg IV every 24h) with either vancomycin (1 g IV every 12h) or an anti-staphylococcal semi-synthetic penicillin (i.e., nafcillin, oxacillin, cloxacillin, or flucloxacillin; 4 to 12 g IV per day). Patients could switch to oral therapy after a minimum of 4 days of IV treatment if clinical improvement was demonstrated. Patients known to have bacteremia at baseline were excluded. Patients with creatinine clearance (CLCR) between 30 and 70 mL/min were to receive a lower dose of daptomycin for injection as specified in the protocol; however, the majority of patients in this subpopulation did not have the dose of daptomycin for injection adjusted.

Table 15. Investigator’s Primary Diagnosis in the cSSSI Trials in Adult Patients (Population: ITT)
Primary Diagnosis | Adult Patients (Daptomycin for Injection / Comparator [Comparator: vancomycin (1 g IV every 12h) or an anti-staphylococcal semi-synthetic penicillin (i.e., nafcillin, oxacillin, cloxacillin, or flucloxacillin; 4 to 12 g/day IV in divided doses).])
 | Study 9801; N=264 / N=266 | Study 9901; N=270 / N=292 | Pooled; N=534 / N=558
Wound Infection | 99 (38%) / 116 (44%) | 102 (38%) / 108 (37%) | 201 (38%) / 224 (40%)
Major Abscess | 55 (21%) / 43 (16%) | 59 (22%) / 65 (22%) | 114 (21%) / 108 (19%)
Ulcer Infection | 71 (27%) / 75 (28%) | 53 (20%) / 68 (23%) | 124 (23%) / 143 (26%)
Other Infection [The majority of cases were subsequently categorized as complicated cellulitis, major abscesses, or traumatic wound infections.] | 39 (15%) / 32 (12%) | 56 (21%) / 51 (18%) | 95 (18%) / 83 (15%)

One trial was conducted primarily in the United States and South Africa (study 9801), and the second was conducted at non-US sites only (study 9901). The two trials were similar in design but differed in patient characteristics, including history of diabetes and peripheral vascular disease. There were a total of 534 adult patients treated with daptomycin for injection and 558 treated with comparator in the two trials. The majority (89.7%) of patients received IV medication exclusively.

The efficacy endpoints in both trials were the clinical success rates in the intent-to-treat (ITT) population and in the clinically evaluable (CE) population. In study 9801, clinical success rates in the ITT population were 62.5% (165/264) in patients treated with daptomycin for injection and 60.9% (162/266) in patients treated with comparator drugs. Clinical success rates in the CE population were 76.0% (158/208) in patients treated with daptomycin for injection and 76.7% (158/206) in patients treated with comparator drugs. In study 9901, clinical success rates in the ITT population were 80.4% (217/270) in patients treated with daptomycin for injection and 80.5% (235/292) in patients treated with comparator drugs. Clinical success rates in the CE population were 89.9% (214/238) in patients treated with daptomycin for injection and 90.4% (226/250) in patients treated with comparator drugs.

The success rates by pathogen for microbiologically evaluable patients are presented in Table 16.

Table 16. Clinical Success Rates by Infecting Pathogen in the cSSSI Trials in Adult Patients (Population: Microbiologically Evaluable)
Pathogen | Success Rate n/N (%)
 | Daptomycin for Injection | Comparator [Comparator: vancomycin (1 g IV every 12h) or an anti-staphylococcal semi-synthetic penicillin (i.e., nafcillin, oxacillin, cloxacillin, or flucloxacillin; 4 to 12 g/day IV in divided doses).]
Methicillin-susceptible Staphylococcus aureus (MSSA) [As determined by the central laboratory.] | 170/198 (86%) | 180/207 (87%)
Methicillin-resistant Staphylococcus aureus (MRSA) | 21/28 (75%) | 25/36 (69%)
Streptococcus pyogenes | 79/84 (94%) | 80/88 (91%)
Streptococcus agalactiae | 23/27 (85%) | 22/29 (76%)
Streptococcus dysgalactiae subsp. equisimilis | 8/8 (100%) | 9/11 (82%)
Enterococcus faecalis (vancomycin-susceptible only) | 27/37 (73%) | 40/53 (76%)

Pediatric Patients (1 to 17 Years of Age) with cSSSI

The cSSSI pediatric trial was a single prospective multi-center, randomized, comparative trial. A total of 396 pediatric patients aged 1 to 17 years with cSSSI caused by Gram positive pathogens were enrolled into the study. Patients known to have bacteremia, osteomyelitis, endocarditis, and pneumonia at baseline were excluded. Patients were enrolled in a stepwise approach into four age groups and given age-dependent doses of daptomycin for injection once daily for up to 14 days. The different age groups and doses evaluated were as follows: Adolescents (12 to 17 years) treated with 5 mg/kg of daptomycin for injection (n=113), Children (7 to 11 years) treated with 7 mg/kg of daptomycin for injection (n=113), Children (2 to 6 years) treated with 9 mg/kg of daptomycin for injection (n=125) and Infants (1 to <2 years) treated with 10 mg/kg (n= 45).

Patients were randomized 2:1 to receive daptomycin for injection or a standard of care (SOC) comparator, which included intravenous therapy with either vancomycin, clindamycin, or an anti-staphylococcal semi-synthetic penicillin (nafcillin, oxacillin, or cloxacillin). Patients could switch to oral therapy after clinical improvement was demonstrated (no minimum IV dosing was required).

The primary objective of this study was to evaluate the safety of daptomycin for injection. The clinical outcome was determined by resolution or improvement of symptoms at the End-of-Treatment (EOT), 3 days after the last dose, and Test-of-Cure (TOC), 7-14 days after the last dose. Investigator observed outcomes were verified in a blinded fashion. Of the 396 subjects randomized in the study, 389 subjects were treated with daptomycin for injection or comparator and included in the ITT population. Of these, 257 subjects were randomized to the daptomycin for injection group and 132 subjects were randomized to the comparator group. Approximately 95% of subjects switched to oral therapy. The mean day of switch was day 4, and ranged from day 1 to day 14. The clinical success rates determined at 7–14 days after last dose of therapy (IV and oral) (TOC visit) were 88% (227/257) for daptomycin for injection and 86% (114/132) for comparator.

14.2 S. aureus Bacteremia/Endocarditis

Adults with S. aureus Bacteremia/Endocarditis

The efficacy of daptomycin for injection in the treatment of adult patients with S. aureus bacteremia was demonstrated in a randomized, controlled, multinational, multicenter, open-label trial. In this trial, adult patients with at least one positive blood culture for S. aureus obtained within 2 calendar days prior to the first dose of study drug and irrespective of source were enrolled and randomized to either daptomycin for injection (6 mg/kg IV every 24h) or standard of care [an anti-staphylococcal semi-synthetic penicillin 2 g IV every 4h (nafcillin, oxacillin, cloxacillin, or flucloxacillin) or vancomycin 1 g IV every 12h, each with initial gentamicin 1 mg/kg IV every 8 hours for first 4 days]. Of the patients in the comparator group, 93% received initial gentamicin for a median of 4 days, compared with 1 patient (<1%) in the daptomycin for injection group. Patients with prosthetic heart valves, intravascular foreign material that was not planned for removal within 4 days after the first dose of study medication, severe neutropenia, known osteomyelitis, polymicrobial bloodstream infections, creatinine clearance <30 mL/min, and pneumonia were excluded.

Upon entry, patients were classified for likelihood of endocarditis using the modified Duke criteria (Possible, Definite, or Not Endocarditis). Echocardiography, including a transesophageal echocardiogram (TEE), was performed within 5 days following study enrollment. The choice of comparator agent was based on the oxacillin susceptibility of the S. aureus isolate. The duration of study treatment was based on the investigator’s clinical diagnosis. Final diagnoses and outcome assessments at Test of Cure (6 weeks after the last treatment dose) were made by a treatment-blinded Adjudication Committee, using protocol-specified clinical definitions and a composite primary efficacy endpoint (clinical and microbiological success) at the Test of Cure visit.

A total of 246 patients ≥18 years of age (124 daptomycin for injection, 122 comparator) with S. aureus bacteremia were randomized from 48 centers in the US and Europe. In the ITT population, 120 patients received daptomycin for injection and 115 received comparator (62 received an anti-staphylococcal semi-synthetic penicillin and 53 received vancomycin). Thirty-five patients treated with an anti-staphylococcal semi-synthetic penicillin received vancomycin initially for 1 to 3 days, pending final susceptibility results for the S. aureus isolates. The median age among the 235 patients in the ITT population was 53 years (range: 21 to 91 years); 30/120 (25%) in the daptomycin for injection group and 37/115 (32%) in the comparator group were ≥65 years of age. Of the 235 ITT patients, there were 141 (60%) males and 156 (66%) Caucasians across the two treatment groups. In addition, 176 (75%) of the ITT population had systemic inflammatory response syndrome (SIRS) at baseline and 85 (36%) had surgical procedures within 30 days prior to onset of the S. aureus bacteremia. Eighty-nine patients (38%) had bacteremia caused by methicillin-resistant S. aureus (MRSA). Entry diagnosis was based on the modified Duke criteria and comprised 37 (16%) Definite, 144 (61%) Possible, and 54 (23%) Not Endocarditis. Of the 37 patients with an entry diagnosis of Definite Endocarditis, all (100%) had a final diagnosis of infective endocarditis, and of the 144 patients with an entry diagnosis of Possible Endocarditis, 15 (10%) had a final diagnosis of infective endocarditis as assessed by the Adjudication Committee. Of the 54 patients with an entry diagnosis of Not Endocarditis, 1 (2%) had a final diagnosis of infective endocarditis as assessed by the Adjudication Committee.

In the ITT population, there were 182 patients with bacteremia and 53 patients with infective endocarditis as assessed by the Adjudication Committee, including 35 with right-sided endocarditis and 18 with left-sided endocarditis. The 182 patients with bacteremia comprised 121 with complicated S. aureus bacteremia and 61 with uncomplicated S. aureus bacteremia.

Complicated bacteremia was defined as S. aureus isolated from blood cultures obtained on at least 2 different calendar days, and/or metastatic foci of infection (deep tissue involvement), and classification of the patient as not having endocarditis according to the modified Duke criteria. Uncomplicated bacteremia was defined as S. aureus isolated from blood culture(s) obtained on a single calendar day, no metastatic foci of infection, no infection of prosthetic material, and classification of the patient as not having endocarditis according to the modified Duke criteria. The definition of right-sided infective endocarditis (RIE) used in the clinical trial was Definite or Possible Endocarditis according to the modified Duke criteria and no echocardiographic evidence of predisposing pathology or active involvement of either the mitral or aortic valve. Complicated RIE comprised patients who were not intravenous drug users, had a positive blood culture for MRSA, serum creatinine ≥2.5 mg/dL, or evidence of extrapulmonary sites of infection. Patients who were intravenous drug users, had a positive blood culture for methicillin-susceptible S. aureus (MSSA), had serum creatinine <2.5 mg/dL, and were without evidence of extrapulmonary sites of infection were considered to have uncomplicated RIE.

The coprimary efficacy endpoints in the trial were the Adjudication Committee success rates at the Test of Cure visit (6 weeks after the last treatment dose) in the ITT and Per Protocol (PP) populations. The overall Adjudication Committee success rates in the ITT population were 44.2% (53/120) in patients treated with daptomycin for injection and 41.7% (48/115) in patients treated with comparator (difference = 2.4% [95% CI −10.2, 15.1]).

The success rates in the PP population were 54.4% (43/79) in patients treated with daptomycin for injection and 53.3% (32/60) in patients treated with comparator (difference = 1.1% [95% CI −15.6, 17.8]).

Adjudication Committee success rates are shown in Table 17.

Table 17. Adjudication Committee Success Rates at Test of Cure in the S. aureus Bacteremia/Endocarditis Trial in Adult Patients (Population: ITT)
Population | Success Rate n/N (%) |  | Difference: Daptomycin for Injection −Comparator (Confidence Interval)
 | Daptomycin for Injection 6 mg/kg | Comparator [Comparator: vancomycin (1 g IV every 12h) or an anti-staphylococcal semi-synthetic penicillin (i.e., nafcillin, oxacillin, cloxacillin, or flucloxacillin; 2 g IV every 4h), each with initial low-dose gentamicin.]
Overall | 53/120 (44%) | 48/115 (42%) | 2.4% (−10.2, 15.1) [95% Confidence Interval]
Baseline Pathogen
Methicillin-susceptible S. aureus | 33/74 (45%) | 34/70 (49%) | −4.0% (−22.6, 14.6) [97.5% Confidence Interval (adjusted for multiplicity)]
Methicillin-resistant S. aureus | 20/45 (44%) | 14/44 (32%) | 12.6% (−10.2, 35.5)
Entry Diagnosis [According to the modified Duke criteria^5]
Definite or Possible Infective Endocarditis | 41/90 (46%) | 37/91 (41%) | 4.9% (−11.6, 21.4)
Not Infective Endocarditis | 12/30 (40%) | 11/24 (46%) | −5.8% (−36.2, 24.5)
Final Diagnosis
Uncomplicated Bacteremia | 18/32 (56%) | 16/29 (55%) | 1.1% (−31.7, 33.9) [99% Confidence Interval (adjusted for multiplicity)]
Complicated Bacteremia | 26/60 (43%) | 23/61 (38%) | 5.6% (−17.3, 28.6)
Right-Sided Infective Endocarditis | 8/19 (42%) | 7/16 (44%) | −1.6% (−44.9, 41.6)
Uncomplicated Right-Sided Infective Endocarditis | 3/6 (50%) | 1/4 (25%) | 25.0% (−51.6, 100.0)
Complicated Right-Sided Infective Endocarditis | 5/13 (39%) | 6/12 (50%) | −11.5% (−62.4, 39.4)
Left-Sided Infective Endocarditis | 1/9 (11%) | 2/9 (22%) | −11.1% (−55.9, 33.6)

Eighteen (18/120) patients in the daptomycin for injection arm and 19/116 patients in the comparator arm died during the trial. These comprise 3/28 daptomycin for injection-treated patients and 8/26 comparator-treated patients with endocarditis, as well as 15/92 daptomycin for injection-treated patients and 11/90 comparator-treated patients with bacteremia. Among patients with persisting or relapsing S. aureus infections, 8/19 daptomycin for injection-treated patients and 7/11 comparator-treated patients died.

Overall, there was no difference in time to clearance of S. aureus bacteremia between daptomycin for injection and comparator. The median time to clearance in patients with MSSA was 4 days and in patients with MRSA was 8 days.

Failure of treatment due to persisting or relapsing S. aureus infections was assessed by the Adjudication Committee in 19/120 (16%) daptomycin for injection-treated patients (12 with MRSA and 7 with MSSA) and 11/115 (10%) comparator-treated patients (9 with MRSA treated with vancomycin and 2 with MSSA treated with an anti-staphylococcal semi-synthetic penicillin). Among all failures, isolates from 6 daptomycin for injection-treated patients and 1 vancomycin-treated patient developed increasing MICs (reduced susceptibility) by central laboratory testing during or following therapy. Most patients who failed due to persisting or relapsing S. aureus infection had deep-seated infection and did not receive necessary surgical intervention [see Warnings and Precautions (5.9)].

Pediatric Patients (1 to 17 Years of Age) with S. aureus Bacteremia

The pediatric S. aureus bacteremia study was designed as a prospective multi-center, randomized, comparative trial to treat pediatric patients aged 1 to 17 years with bacteremia. Patients known to have endocarditis or pneumonia at baseline were excluded. Patients were enrolled in a stepwise approach into three age groups and given age-dependent doses of daptomycin for injection once daily for up to 42 days. The different age groups and doses evaluated were as follows: Adolescents (12 to 17 years, n=14 patients) treated with daptomycin for injection dosed at 7 mg/kg once daily, Children (7 to 11 years, n=19 patients) treated with daptomycin for injection dosed at 9 mg/kg once daily and Children (2 to 6 years, n=22 patients) treated with daptomycin for injection dosed at 12 mg/kg once daily. No patients 1 to <2 years of age were enrolled.

Patients were randomized 2:1 to receive daptomycin for injection or a standard of care comparator, which included intravenous therapy with vancomycin, semi-synthetic penicillin, first generation cephalosporin or clindamycin. Patients could switch to oral therapy after clinical improvement was demonstrated (no minimum IV dosing was required).

The primary objective of this study was to assess the safety of daptomycin for injection. The clinical outcome was determined by resolution or improvement of symptoms at test-of-cure (TOC) visit, 7 to 14 days after the last dose, which was assessed by the site level Blinded Evaluator.

Of the 82 subjects randomized in the study, 81 subjects were treated with daptomycin for injection or comparator and included in the safety population, and 73 had a proven S. aureus bacteremia at Baseline. Of these, 51 subjects were randomized to the daptomycin for injection group and 22 subjects were randomized to the comparator group. The mean duration of IV therapy was 12 days, with a range of 1 to 44 days. Forty-eight subjects switched to oral therapy, and the mean duration of oral therapy was 21 days. The clinical success rates determined at 7 to 14 days after last dose of therapy (IV and oral) (TOC visit) were 88% (45/51) for daptomycin for injection and 77% (17/22) for comparator.

15 REFERENCES

1. Liu SL, Howard LC, Van Lier RBL, Markham JK: Teratology studies with daptomycin administered intravenously (iv) to rats and rabbits. Teratology 37(5):475, 1988.
2. Stroup JS, Wagner J, Badzinski T: Use of daptomycin in a pregnant patient with Staphylococcus aureus endocarditis. Ann Pharmacother 44(4):746-749, 2010.
3. Buitrago MI, Crompton JA, Bertolami S, North DS, Nathan RA. Extremely low excretion of daptomycin into breast milk of a nursing mother with methicillin-resistant Staphylococcus aureus pelvic inflammatory disease. Pharmacotherapy 2009;29(3):347–351.
4. Klibanov OM, Vickery S, Nortey C: Successful treatment of infective panniculitis with daptomycin in a pregnant, morbidly obese patient. Ann Pharmacother 48(5):652-655, 2014.
5. Li JS, Sexton DJ, Mick N, Nettles R, Fowler VG Jr, Ryan T, Bashore T, Corey GR. Proposed modifications to the Duke criteria for the diagnosis of infective endocarditis. Clin Infect Dis 2000;30:633–638.

16 HOW SUPPLIED/STORAGE AND HANDLING

Daptomycin in Sodium Chloride Injection is supplied as a single-dose premixed frozen isosmotic sterile, nonpyrogenic solution in 50 mL or 100 mL GALAXY plastic containers as follows:

Code | Product Description | NDC Number
2G3593 | 350 milligrams daptomycin in 50 mL (7 mg/mL); Supplied as 24 bags per carton | 0338-0712-24
2G3594 | 500 milligrams daptomycin in 50 mL (10 mg/mL); Supplied as 24 bags per carton | 0338-0714-24
2G3595 | 700 milligrams daptomycin in 100 mL (7 mg/mL); Supplied as 12 bags per carton | 0338-0716-12
2G3596 | 1,000 milligrams daptomycin in 100 mL (10 mg/mL); Supplied as 12 bags per carton | 0338-0718-12

Store in a freezer capable of maintaining a temperature of -20°C (-4°F) or below [see Dosage and Administration (2.7)].

Handle frozen product containers with care. Product containers may be fragile in the frozen state

17 PATIENT COUNSELING INFORMATION

Allergic Reactions

Advise patients that allergic reactions, including serious skin, kidney, lung, or other organ reactions, could occur and that these serious reactions require immediate treatment. Patients should report any previous allergic reactions to daptomycin [see Warnings and Precautions (5.1, 5.4, 5.5)].

Muscle Pain or Weakness (Myopathy and Rhabdomyolysis, Peripheral Neuropathy)

Advise patients to report muscle pain or weakness, especially in the forearms and lower legs, as well as tingling or numbness [see Warnings and Precautions (5.2, 5.6)].

Cough, Breathlessness or Fever (Eosinophilic Pneumonia)

Advise patients to report any symptoms of cough, breathlessness, or fever [see Warnings and Precautions (5.3)].

C. difficile-Associated Diarrhea (CDAD)

Advise patients that diarrhea is a common problem caused by antibacterials including daptomycin for injection that usually ends when the antibacterial is discontinued. Sometimes after starting treatment with antibacterials, including Daptomycin in Sodium Chloride Injection, patients can develop watery and bloody stools (with or without stomach cramps and fever), even as late as 2 or more months after having received the last dose of the antibacterial. If this occurs, patients should contact their physician as soon as possible [see Warnings and Precautions (5.8)].

Antibacterial Resistance

Patients should be counseled that antibacterial drugs, including Daptomycin in Sodium Chloride Injection, should be used to treat bacterial infections. They do not treat viral infections (e.g., the common cold). When Daptomycin in Sodium Chloride Injection is prescribed to treat a bacterial infection, patients should be told that although it is common to feel better early in the course of therapy, the medication should be administered exactly as directed. Skipping doses or not completing the full course of therapy may (1) decrease the effectiveness of the immediate treatment and (2) increase the likelihood that bacteria will develop resistance and will not be treatable by Daptomycin in Sodium Chloride Injection or other antibacterial drugs in the future.

Baxter Logo
Baxter Healthcare Corporation
Deerfield, IL 60015 USA

Made in the USA

Baxter and Galaxy are registered trademarks of Baxter International Inc.

07-19-09-230

PACKAGE/LABEL PRINCIPAL DISPLAY PANEL

Container Label

DAPTOmycin
in 0.9% Sodium Chloride Injection
350 mg per 50 mL (7mg/mL)

350 mg
TOTAL

NDC 0338-0712-24
50 mL Single Dose Container
Discard unused portion

Code 2G3593
Sterile Nonpyrogenic
For Intravenous Infusion Only

Each 50 mL contains: 350 mg Daptomycin, 450 mg Sodium Chloride, USP,
25 mg Monobasic Sodium Phosphate Monohydrate, USP, 27.5 mg Dibasic
Sodium Phosphate Anhydrous, USP and Water for Injection, USP. pH may
have been adjusted with Sodium Hydroxide and/or Hydrochloric Acid.
Cautions: Do not add supplementary medication or additives.
Recommended Dosage: See prescribing information. Rx only
Store frozen at or below -20°C/-4°F. Do not force thaw. Thaw at room
temperature (25°C/77°F) or under refrigeration (5°C/41°F). Product should
not be thawed by immersion in water baths or by microwave irradiation.
Thawed solution is stable for 30 days under refrigeration or 48 hours at room
temperature. Do not refreeze.

GALAXY

Baxter Logo
Baxter Healthcare Corporation, Deerfield, IL 60015 USA
Baxter and Galaxy are registered trademarks of Baxter International Inc.
Made in USA

07-34-00-1224

BAR CODE
3 0338071224 3

Container Label

DAPTOmycin
in 0.9% Sodium Chloride Injection
500 mg per 50 mL (10mg/mL)

500 mg
TOTAL

NDC 0338-0714-24
50 mL Single Dose Container
Discard unused portion

Code 2G3594
Sterile Nonpyrogenic
For Intravenous Infusion Only

Each 50 mL contains: 500 mg Daptomycin, 450 mg Sodium Chloride, USP,
25 mg Monobasic Sodium Phosphate Monohydrate, USP, 27.5 mg Dibasic
Sodium Phosphate Anhydrous, USP and Water for Injection, USP. pH may
have been adjusted with Sodium Hydroxide and/or Hydrochloric Acid.
Cautions: Do not add supplementary medication or additives.
Recommended Dosage: See prescribing information. Rx only
Store frozen at or below -20°C/-4°F. Do not force thaw. Thaw at room
temperature (25°C/77°F) or under refrigeration (5°C/41°F). Product should
not be thawed by immersion in water baths or by microwave irradiation.
Thawed solution is stable for 30 days under refrigeration or 48 hours at room
temperature. Do not refreeze.

GALAXY

Baxter Logo
Baxter Healthcare Corporation, Deerfield, IL 60015 USA
Baxter and Galaxy are registered trademarks of Baxter International Inc.
Made in USA

07-34-00-1225

BAR CODE
3 0338071424 7

Container Label

DAPTOmycin
in 0.9% Sodium Chloride Injection
700 mg per 100 mL (7mg/mL)

700 mg
TOTAL

NDC 0338-0716-12
100 mL Single Dose Container
Discard unused portion

Code 2G3595
Sterile Nonpyrogenic
For Intravenous Infusion Only

Each 100 mL contains: 700 mg Daptomycin, 900 mg Sodium Chloride, USP,
50 mg Monobasic Sodium Phosphate Monohydrate, USP, 55 mg Dibasic
Sodium Phosphate Anhydrous, USP and Water for Injection, USP. pH may
have been adjusted with Sodium Hydroxide and/or Hydrochloric Acid.
Cautions: Do not add supplementary medication or additives.
Recommended Dosage: See prescribing information. Rx only
Store frozen at or below -20°C/-4°F. Do not force thaw. Thaw at room
temperature (25°C/77°F) or under refrigeration (5°C/41°F). Product should
not be thawed by immersion in water baths or by microwave irradiation.
Thawed solution is stable for 30 days under refrigeration or 48 hours at room
temperature. Do not refreeze.

GALAXY

Baxter Logo
Baxter Healthcare Corporation, Deerfield, IL 60015 USA
Baxter and Galaxy are registered trademarks of Baxter International Inc.
Made in USA

07-34-00-1901

BAR CODE
3 0338071612 8

Container Label

DAPTOmycin
in 0.9% Sodium Chloride Injection
1,000 mg per 100 mL (10mg/mL)

1,000 mg
TOTAL

NDC 0338-0718-12
100 mL Single Dose Container
Discard unused portion

Code 2G3596
Sterile Nonpyrogenic
For Intravenous Infusion Only

Each 100 mL contains: 1,000 mg Daptomycin, 900 mg Sodium Chloride, USP,
50 mg Monobasic Sodium Phosphate Monohydrate, USP, 55 mg Dibasic
Sodium Phosphate Anhydrous, USP and Water for Injection, USP. pH may
have been adjusted with Sodium Hydroxide and/or Hydrochloric Acid.
Cautions: Do not add supplementary medication or additives.
Recommended Dosage: See prescribing information. Rx only
Store frozen at or below -20°C/-4°F. Do not force thaw. Thaw at room
temperature (25°C/77°F) or under refrigeration (5°C/41°F). Product should
not be thawed by immersion in water baths or by microwave irradiation.
Thawed solution is stable for 30 days under refrigeration or 48 hours at room
temperature. Do not refreeze.

GALAXY

Baxter Logo
Baxter Healthcare Corporation, Deerfield, IL 60015 USA
Baxter and Galaxy are registered trademarks of Baxter International Inc.
Made in USA

07-34-00-1902

BAR CODE
3 0338071812 2

Carton Label

Store frozen at or below -20°C/-4°F. Do not force thaw. Do not refreeze. Thaw at room temperature (25°C/77°F)
or under refrigeration (5°C/41°F). Product should not be thawed by immersion in water baths or by microwave
irradiation. Thawed solution is stable for 30 days under refrigeration or 48 hours at room temperature. Handle frozen
product containers with care. Product containers may be fragile in the frozen state.
Baxter and Galaxy are registered trademarks of Baxter International Inc.
GALAXY

07-04-00-0501

DAPTOmycin
in 0.9% Sodium Chloride Injection
350 mg per 50 mL (7 mg/mL)

350 mg
TOTAL

Baxter Logo
12 – 50 mL Single Dose Containers
Sterile – Nonpyrogenic
For Intravenous Infusion Only
Store at or below -20°C/-4°F.

NDC 0338-0712-24
Code 2G3593
BAR CODE
(01) 20303380712247

Each 50 mL contains: 350 mg Daptomycin, 450 mg Sodium Chloride, USP, 25 mg Monobasic Sodium Phosphate Monohydrate, USP, 27.5 mg Dibasic Sodium Phosphate Anhydrous, USP and Water for Injection, USP. pH may have
been adjusted with Sodium Hydroxide and/or Hydrochloric Acid.
Cautions: Do not add supplementary medications or additives.
Recommended Dosage: See prescribing information. Rx only.

Baxter Healthcare Corporation Deerfield, IL 60015 USA

Carton Label

Store frozen at or below -20°C/-4°F. Do not force thaw. Do not refreeze. Thaw at room temperature (25°C/77°F)
or under refrigeration (5°C/41°F). Product should not be thawed by immersion in water baths or by microwave
irradiation. Thawed solution is stable for 30 days under refrigeration or 48 hours at room temperature. Handle frozen
product containers with care. Product containers may be fragile in the frozen state.
Baxter and Galaxy are registered trademarks of Baxter International Inc.
GALAXY

07-04-00-0502

DAPTOmycin
in 0.9% Sodium Chloride Injection
500 mg per 50 mL (10 mg/mL)

500 mg
TOTAL

Baxter Logo
12 – 50 mL Single Dose Containers
Sterile – Nonpyrogenic
For Intravenous Infusion Only
Store at or below -20°C/-4°F.

NDC 0338-0714-24
Code 2G3594
Bar Code
(01) 20303380714241

Each 50 mL contains: 500 mg Daptomycin, 450 mg Sodium Chloride, USP, 25 mg Monobasic Sodium Phosphate Monohydrate, USP, 27.5 mg Dibasic Sodium Phosphate Anhydrous, USP and Water for Injection, USP. pH may have
been adjusted with Sodium Hydroxide and/or Hydrochloric Acid.
Cautions: Do not add supplementary medications or additives.
Recommended Dosage: See prescribing information. Rx only.

Baxter Healthcare Corporation Deerfield, IL 60015 USA

Carton Label

Store frozen at or below -20°C/-4°F. Do not force thaw. Do not refreeze. Thaw at room temperature (25°C/77°F)
or under refrigeration (5°C/41°F). Product should not be thawed by immersion in water baths or by microwave
irradiation. Thawed solution is stable for 30 days under refrigeration or 48 hours at room temperature. Handle frozen
product containers with care. Product containers may be fragile in the frozen state.
Baxter and Galaxy are registered trademarks of Baxter International Inc.
GALAXY

07-04-00-0503

DAPTOmycin
in 0.9% Sodium Chloride Injection
700 mg per 100 mL (7 mg/mL)

700 mg
TOTAL

Baxter Logo
6 – 100 mL Single Dose Containers
Sterile – Nonpyrogenic
For Intravenous Infusion Only
Store at or below -20°C/-4°F.

NDC 0338-0716-12
Code 2G3595
Bar Code
(01) 20303380716122

Each 100 mL contains: 700 mg Daptomycin, 900 mg Sodium Chloride, USP, 50 mg Monobasic Sodium Phosphate Monohydrate, USP, 55 mg Dibasic Sodium Phosphate Anhydrous, USP and Water for Injection, USP. pH may have been
adjusted with Sodium Hydroxide and/or Hydrochloric Acid.
Cautions: Do not add supplementary medications or additives.
Recommended Dosage: See prescribing information. Rx only.

Baxter Healthcare Corporation Deerfield, IL 60015 USA

Carton Label

Store frozen at or below -20°C/-4°F. Do not force thaw. Do not refreeze. Thaw at room temperature (25°C/77°F)
or under refrigeration (5°C/41°F). Product should not be thawed by immersion in water baths or by microwave
irradiation. Thawed solution is stable for 30 days under refrigeration or 48 hours at room temperature. Handle frozen
product containers with care. Product containers may be fragile in the frozen state.
Baxter and Galaxy are registered trademarks of Baxter International Inc.
GALAXY

07-04-00-0504

DAPTOmycin
in 0.9% Sodium Chloride Injection
1,000 mg per 100 mL (10 mg/mL)

1,000 mg
TOTAL

Baxter Logo
6 – 100 mL Single Dose Containers
Sterile – Nonpyrogenic
For Intravenous Infusion Only
Store at or below -20°C/-4°F.

NDC 0338-0718-12
Code 2G3596
Bar Code
(01) 20303380718126

Each 100 mL contains: 1000 mg Daptomycin, 900 mg Sodium Chloride, USP, 50 mg Monobasic Sodium Phosphate Monohydrate, USP, 55 mg Dibasic Sodium Phosphate Anhydrous, USP and Water for Injection, USP. pH may have been
adjusted with Sodium Hydroxide and/or Hydrochloric Acid.
Cautions: Do not add supplementary medications or additives.
Recommended Dosage: See prescribing information. Rx only.

Baxter Healthcare Corporation Deerfield, IL 60015 USA